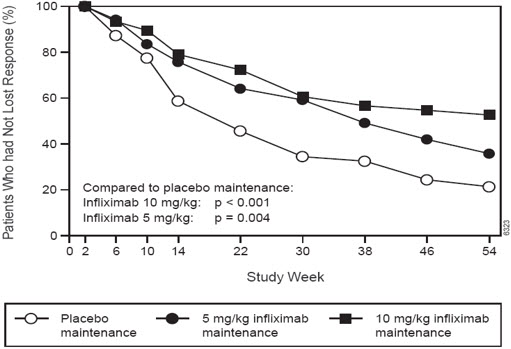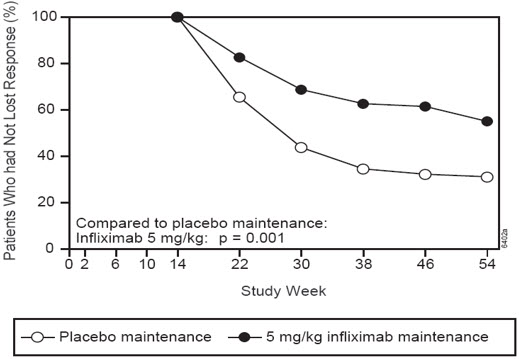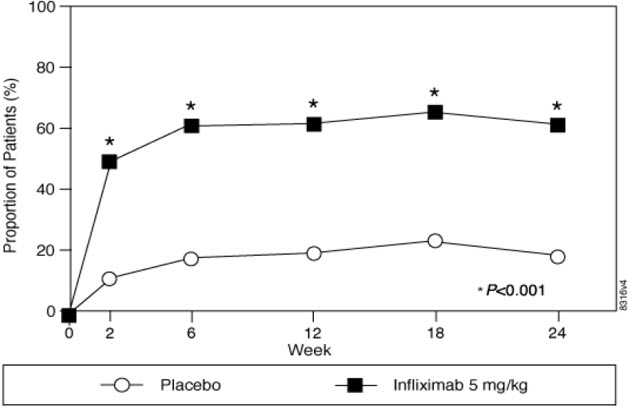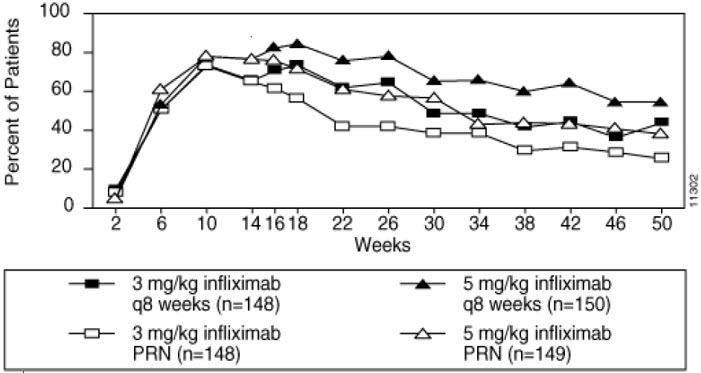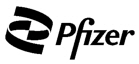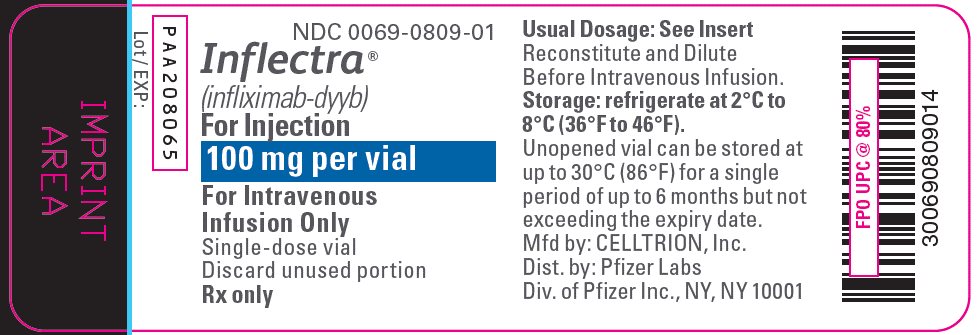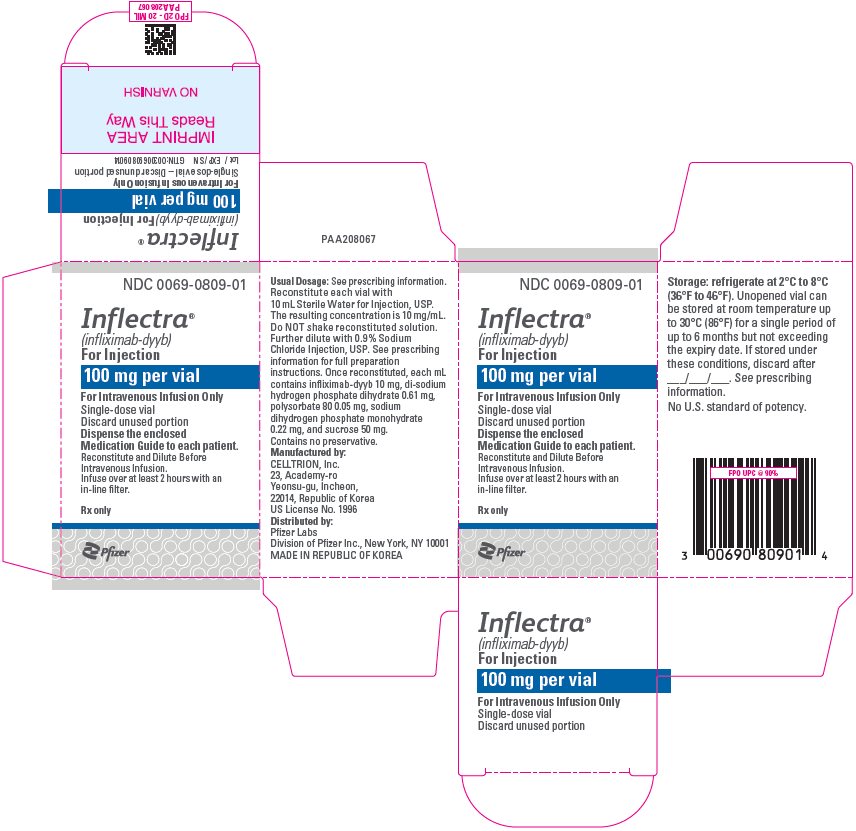 DRUG LABEL: INFLECTRA
NDC: 0069-0809 | Form: INJECTION, POWDER, LYOPHILIZED, FOR SOLUTION
Manufacturer: Pfizer Laboratories Div Pfizer Inc
Category: prescription | Type: HUMAN PRESCRIPTION DRUG LABEL
Date: 20250910

ACTIVE INGREDIENTS: INFLIXIMAB 100 mg/10 mL
INACTIVE INGREDIENTS: SUCROSE 500 mg/10 mL; POLYSORBATE 80 0.5 mg/10 mL; SODIUM PHOSPHATE, MONOBASIC, MONOHYDRATE 2.2 mg/10 mL; SODIUM PHOSPHATE, DIBASIC, DIHYDRATE 6.1 mg/10 mL

HIGHLIGHTS OF PRESCRIBING INFORMATION

These highlights do not include all the information needed to use INFLECTRA safely and effectively. See full prescribing information for INFLECTRA.
INFLECTRA® (infliximab-dyyb) for injection, for intravenous use
Initial U.S. Approval: 2016
INFLECTRA (infliximab-dyyb) is biosimilar [Biosimilar means that the biological product is approved based on data demonstrating that it is highly similar to an FDA-approved biological product, known as a reference product, and that there are no clinically meaningful differences between the biosimilar product and the reference product. Biosimilarity of INFLECTRA has been demonstrated for the condition(s) of use (e.g., indication(s), dosing regimen(s)), strength(s), dosage form(s), and route(s) of administration described in its Full Prescribing Information.] to REMICADE (infliximab)

WARNING: SERIOUS INFECTIONS and MALIGNANCY

See full prescribing information for complete boxed warning

- Increased risk of serious infections leading to hospitalization or death, including tuberculosis (TB), bacterial sepsis, invasive fungal infections (such as histoplasmosis) and infections due to other opportunistic pathogens. (5.1)
- Discontinue INFLECTRA if a patient develops a serious infection.
- Perform test for latent TB; if positive, start treatment for TB prior to starting INFLECTRA. Monitor all patients for active TB during treatment, even if initial latent TB test is negative. (5.1)
- Lymphoma and other malignancies, some fatal, have been reported in children and adolescent patients treated with tumor necrosis factor (TNF) blockers, including infliximab products. (5.2)
- Postmarketing cases of fatal hepatosplenic T-cell lymphoma (HSTCL) have been reported in patients treated with TNF blockers, including infliximab products. Almost all had received azathioprine or 6-mercaptopurine concomitantly with a TNF blocker at or prior to diagnosis. The majority of cases were reported in patients with Crohn's disease or ulcerative colitis, most of whom were adolescent or young adult males. (5.2)

1 INDICATIONS AND USAGE

INFLECTRA is a tumor necrosis factor (TNF) blocker indicated for:

Crohn's Disease (1.1):

- reducing signs and symptoms and inducing and maintaining clinical remission in adult patients with moderately to severely active disease who have had an inadequate response to conventional therapy.
- reducing the number of draining enterocutaneous and rectovaginal fistulas and maintaining fistula closure in adult patients with fistulizing disease.

Pediatric Crohn's Disease (1.2):

- reducing signs and symptoms and inducing and maintaining clinical remission in pediatric patients 6 years of age and older with moderately to severely active disease who have had an inadequate response to conventional therapy.

Ulcerative Colitis (1.3):

- reducing signs and symptoms, inducing and maintaining clinical remission and mucosal healing, and eliminating corticosteroid use in adult patients with moderately to severely active disease who have had an inadequate response to conventional therapy.

Pediatric Ulcerative Colitis (1.4):

- reducing signs and symptoms and inducing and maintaining clinical remission in pediatric patients 6 years of age and older with moderately to severely active disease who have had an inadequate response to conventional therapy.

Rheumatoid Arthritis (1.5) in combination with methotrexate:

- reducing signs and symptoms, inhibiting the progression of structural damage, and improving physical function in adult patients with moderately to severely active disease.

Ankylosing Spondylitis (1.6):

- reducing signs and symptoms in adult patients with active disease.

Psoriatic Arthritis (1.7):

- reducing signs and symptoms of active arthritis, inhibiting the progression of structural damage, and improving physical function in adult patients.

Plaque Psoriasis (1.8):

- treatment of adult patients with chronic severe (i.e., extensive and/or disabling) plaque psoriasis who are candidates for systemic therapy and when other systemic therapies are medically less appropriate.

2 DOSAGE AND ADMINISTRATION

Prior to treatment, ensure appropriate personnel and medication are available to treat reactions (e.g., hypersensitivity) that occur during infusion and shortly after infusion (2.11)

INFLECTRA is administered by intravenous infusion for at least 2 hours with an in-line filter (2.11)

Crohn's Disease (2.1)

- 5 mg/kg at 0, 2 and 6 weeks, then every 8 weeks. Some adult patients who initially respond to treatment may benefit from increasing the dose to 10 mg/kg every 8 weeks if they later lose their response.

Pediatric Crohn's Disease (≥ 6 years old) (2.2)

- 5 mg/kg at 0, 2 and 6 weeks, then every 8 weeks.

Ulcerative Colitis (2.3)

- 5 mg/kg at 0, 2 and 6 weeks, then every 8 weeks.

Pediatric Ulcerative Colitis (≥ 6 years old) (2.4)

- 5 mg/kg at 0, 2 and 6 weeks, then every 8 weeks.

Rheumatoid Arthritis (2.5)

- In conjunction with methotrexate, 3 mg/kg at 0, 2 and 6 weeks, then every 8 weeks. Some patients may benefit from increasing the dose up to 10 mg/kg every 8 weeks or treating as often as every 4 weeks.

Ankylosing Spondylitis (2.6)

- 5 mg/kg at 0, 2 and 6 weeks, then every 6 weeks.

Psoriatic Arthritis (2.7) and Plaque Psoriasis (2.8)

- 5 mg/kg at 0, 2 and 6 weeks, then every 8 weeks.

3 DOSAGE FORMS AND STRENGTHS

For injection: 100 mg of infliximab-dyyb as a lyophilized powder in a single-dose vial for reconstitution and dilution. (2.11, 3)

4 CONTRAINDICATIONS

- INFLECTRA doses >5 mg/kg in moderate or severe heart failure. (4)
- Previous severe hypersensitivity reaction to infliximab products or any inactive ingredients of INFLECTRA or to any murine proteins. (4)

5 WARNINGS AND PRECAUTIONS

- Serious infections – do not give INFLECTRA during an active infection. If an infection develops, monitor carefully and stop INFLECTRA if infection becomes serious. (5.1)
- Invasive fungal infections – for patients who develop a systemic illness on INFLECTRA, consider empiric antifungal therapy for those who reside or travel to regions where mycoses are endemic. (5.1)
- Malignancies – the incidence of malignancies, including invasive cervical cancer and lymphoma, was greater in infliximab-treated patients than in controls. Due to the risk of HSTCL carefully assess the risk/benefit especially if the patient has Crohn's disease or ulcerative colitis, is male, and is receiving azathioprine or 6-mercaptopurine treatment. (5.2)
- Hepatitis B virus (HBV) reactivation – test for HBV infection before starting INFLECTRA. Monitor HBV carriers during and several months after therapy. If reactivation occurs, stop INFLECTRA and begin anti-viral therapy. (5.3)
- Hepatotoxicity – severe hepatic reactions, some fatal or necessitating liver transplantation. Stop INFLECTRA in cases of jaundice and/or marked liver enzyme elevations. (5.4)
- Heart failure –new onset or worsening symptoms may occur. (4, 5.5)
- Cytopenias – advise patients to seek immediate medical attention if signs and symptoms develop, and consider stopping INFLECTRA. (5.6)
- Hypersensitivity – serious infusion reactions including anaphylaxis or serum sickness-like reactions may occur. (5.7)
- Cardiovascular and Cerebrovascular Reactions – Cerebrovascular accidents, myocardial infarctions (some fatal), and arrhythmias have been reported during and within 24 hours of initiation of infliximab product infusion. Monitor patients during INFLECTRA infusion and if serious reaction occurs, discontinue infusion. (5.8)
- Demyelinating disease –exacerbation or new onset may occur. (5.9)
- Lupus-like syndrome –stop INFLECTRA if syndrome develops. (5.12)
- Vaccinations and Use of Live vaccines/therapeutic infectious agents – Prior to initiating INFLECTRA bring pediatric and adult patients up to date with all vaccinations. Live vaccines or therapeutic infectious agents should not be given with INFLECTRA. At least a six month waiting period following birth is recommended before the administration of live vaccines to infants exposed in utero to infliximab products. (5.13)

6 ADVERSE REACTIONS

Most common adverse reactions (>10%) – infections (e.g. upper respiratory, sinusitis, and pharyngitis), infusion-related reactions, headache, and abdominal pain. (6.1)

To report SUSPECTED ADVERSE REACTIONS, contact CELLTRION, Inc. at 1-800-383-7504 or FDA at 1-800-FDA-1088 or www.fda.gov/medwatch.

7 DRUG INTERACTIONS

Other Biological Products– increased risk of serious infections (7.1)

FULL PRESCRIBING INFORMATION

WARNING: SERIOUS INFECTIONS and MALIGNANCY

SERIOUS INFECTIONS

Patients treated with infliximab products are at increased risk for developing serious infections that may lead to hospitalization or death [see Warnings and Precautions (5.1), Adverse Reactions (6.1)]. Most patients who developed these infections were taking concomitant immunosuppressants such as methotrexate or corticosteroids.

INFLECTRA should be discontinued if a patient develops a serious infection or sepsis.

Reported infections include:

- Active tuberculosis, including reactivation of latent tuberculosis. Patients with tuberculosis have frequently presented with disseminated or extrapulmonary disease. Patients should be tested for latent tuberculosis before INFLECTRA use and during therapy. Treatment for latent infection should be initiated prior to INFLECTRA use.
- Invasive fungal infections, including histoplasmosis, coccidioidomycosis, candidiasis, aspergillosis, blastomycosis, and pneumocystosis. Patients with histoplasmosis or other invasive fungal infections may present with disseminated, rather than localized, disease. Antigen and antibody testing for histoplasmosis may be negative in some patients with active infection. Empiric anti-fungal therapy should be considered in patients at risk for invasive fungal infections who develop severe systemic illness.
- Bacterial, viral and other infections due to opportunistic pathogens, including Legionella and Listeria.

The risks and benefits of treatment with INFLECTRA should be carefully considered prior to initiating therapy in patients with chronic or recurrent infection.

Patients should be closely monitored for the development of signs and symptoms of infection during and after treatment with INFLECTRA, including the possible development of tuberculosis in patients who tested negative for latent tuberculosis infection prior to initiating therapy.

MALIGNANCY

Lymphoma and other malignancies, some fatal, have been reported in children and adolescent patients treated with TNF blockers, including infliximab products [see Warnings and Precautions (5.2)].

Postmarketing cases of hepatosplenic T-cell lymphoma (HSTCL), a rare type of T-cell lymphoma, have been reported in patients treated with TNF blockers including infliximab products. These cases have had a very aggressive disease course and have been fatal. Almost all patients had received treatment with azathioprine or 6-mercaptopurine concomitantly with a TNF blocker at or prior to diagnosis. The majority of reported cases have occurred in patients with Crohn's disease or ulcerative colitis and most were in adolescent and young adult males.

1 INDICATIONS AND USAGE

1.1 Crohn's Disease

INFLECTRA is indicated for:

- reducing signs and symptoms and inducing and maintaining clinical remission in adult patients with moderately to severely active Crohn's disease (CD) who have had an inadequate response to conventional therapy.
- reducing the number of draining enterocutaneous and rectovaginal fistulas and maintaining fistula closure in adult patients with fistulizing CD.

1.2 Pediatric Crohn's Disease

INFLECTRA is indicated for reducing signs and symptoms and inducing and maintaining clinical remission in pediatric patients 6 years of age and older with moderately to severely active CD who have had an inadequate response to conventional therapy.

1.3 Ulcerative Colitis

INFLECTRA is indicated for reducing signs and symptoms, inducing and maintaining clinical remission and mucosal healing, and eliminating corticosteroid use in adult patients with moderately to severely active ulcerative colitis (UC) who have had an inadequate response to conventional therapy.

1.4 Pediatric Ulcerative Colitis

INFLECTRA is indicated for reducing signs and symptoms and inducing and maintaining clinical remission in pediatric patients 6 years of age and older with moderately to severely active UC who have had an inadequate response to conventional therapy.

1.5 Rheumatoid Arthritis

INFLECTRA, in combination with methotrexate, is indicated for reducing signs and symptoms, inhibiting the progression of structural damage, and improving physical function in adult patients with moderately to severely active rheumatoid arthritis (RA).

1.6 Ankylosing Spondylitis

INFLECTRA is indicated for reducing signs and symptoms in adult patients with active ankylosing spondylitis (AS).

1.7 Psoriatic Arthritis

INFLECTRA is indicated for reducing signs and symptoms of active arthritis, inhibiting the progression of structural damage, and improving physical function in adult patients with psoriatic arthritis (PsA).

1.8 Plaque Psoriasis

INFLECTRA is indicated for the treatment of adult patients with chronic severe (i.e., extensive and/or disabling) plaque psoriasis (Ps) who are candidates for systemic therapy and when other systemic therapies are medically less appropriate. INFLECTRA should only be administered to patients who will be closely monitored and have regular follow-up visits with a physician [see Boxed Warning, Warnings and Precautions (5)].

2 DOSAGE AND ADMINISTRATION

2.1 Dosage in Adult Crohn's Disease

The recommended dosage of INFLECTRA is 5 mg/kg given as an intravenous induction regimen at 0, 2 and 6 weeks followed by a maintenance regimen of 5 mg/kg every 8 weeks thereafter for the treatment of adults with moderately to severely active CD or fistulizing CD. For adult patients who respond and then lose their response, consideration may be given to treatment with 10 mg/kg every 8 weeks. Patients who do not respond by Week 14 are unlikely to respond with continued dosing and consideration should be given to discontinue INFLECTRA in these patients.

2.2 Dosage in Pediatric Crohn's Disease

The recommended dosage of INFLECTRA for pediatric patients 6 years and older with moderately to severely active CD is 5 mg/kg given as an intravenous induction regimen at 0, 2 and 6 weeks followed by a maintenance regimen of 5 mg/kg every 8 weeks.

2.3 Dosage in Adult Ulcerative Colitis

The recommended dosage of INFLECTRA is 5 mg/kg given as an intravenous induction regimen at 0, 2 and 6 weeks followed by a maintenance regimen of 5 mg/kg every 8 weeks thereafter for the treatment of adult patients with moderately to severely active UC.

2.4 Dosage in Pediatric Ulcerative Colitis

The recommended dosage of INFLECTRA for pediatric patients 6 years and older with moderately to severely active UC is 5 mg/kg given as an intravenous induction regimen at 0, 2 and 6 weeks followed by a maintenance regimen of 5 mg/kg every 8 weeks.

2.5 Dosage in Rheumatoid Arthritis

The recommended dosage of INFLECTRA is 3 mg/kg given as an intravenous induction regimen at 0, 2 and 6 weeks followed by a maintenance regimen of 3 mg/kg every 8 weeks thereafter for the treatment of moderately to severely active RA. INFLECTRA should be given in combination with methotrexate. For patients who have an incomplete response, consideration may be given to adjusting the dosage up to 10 mg/kg every 8 weeks or treating as often as every 4 weeks bearing in mind that risk of serious infections is increased at higher doses per infusion or more frequent dosing [see Adverse Reactions (6.1)].

2.6 Dosage in Ankylosing Spondylitis

The recommended dosage of INFLECTRA is 5 mg/kg given as an intravenous induction regimen at 0, 2 and 6 weeks followed by a maintenance regimen of 5 mg/kg every 6 weeks thereafter for the treatment of active AS.

2.7 Dosage in Psoriatic Arthritis

The recommended dosage of INFLECTRA is 5 mg/kg given as an intravenous induction regimen at 0, 2 and 6 weeks followed by a maintenance regimen of 5 mg/kg every 8 weeks thereafter for the treatment of PsA. INFLECTRA can be used with or without methotrexate.

2.8 Dosage in Plaque Psoriasis

The recommended dosage of INFLECTRA in adult patients is 5 mg/kg given as an intravenous induction regimen at 0, 2 and 6 weeks followed by a maintenance regimen of 5 mg/kg every 8 weeks thereafter for the treatment of chronic severe (i.e., extensive and/or disabling) Ps.

2.9 Assessment for Latent and Active Tuberculosis

Prior to initiating INFLECTRA and periodically during therapy, patients should be evaluated for active tuberculosis and tested for latent infection [see Warnings and Precautions (5.1)].

2.10 Administration Instructions Regarding Infusion Reactions

Prior to treatment, ensure appropriate personnel and medication are available to treat reactions (e.g., hypersensitivity, other reactions) that occur during infusion and shortly after infusion. Prior to infusion with INFLECTRA, patient may be premedicated with histamine-1 receptor antagonists, histamine-2 receptor antagonists, acetaminophen, and/or corticosteroids [see Warnings and Precautions (5.7)].

For mild to moderate reactions during the infusion, consider slowing or stopping the infusion. Upon resolution of these reactions, may reinitiate at a lower infusion rate and/or with histamine-1 receptor antagonists, histamine-2 receptor antagonists, acetaminophen, and/or corticosteroids. Discontinue the infusion if the mild to moderate reactions reoccur.

Discontinue the infusion if severe hypersensitivity reactions occur during the infusion.

2.11 Reconstitution, Dilution, and Administration Instructions

INFLECTRA is intended for use under the guidance and supervision of a healthcare provider. The supplied lyophilized powder must be reconstituted and diluted prior to administration. The infusion solution should be prepared and administered by a trained medical professional using aseptic technique by the following procedure:

1. Calculate the dose, total volume of reconstituted INFLECTRA solution required and the number of INFLECTRA vials needed. More than one vial may be needed for a full dose.
2. Reconstitute each 100 mg INFLECTRA vial with 10 mL of Sterile Water for Injection, USP, to obtain a concentration of 10 mg/mL, using a syringe equipped with a 21-gauge or smaller needle as follows:
  1. Remove the flip-top from the vial and wipe the top with an alcohol swab.
  2. Insert the syringe needle into the vial through the center of the rubber stopper and direct the stream of Sterile Water for Injection, USP, to the glass wall of the vial. Gently swirl the solution by rotating the vial to dissolve the lyophilized powder, which has a cake-like appearance. Avoid prolonged or vigorous agitation. DO NOT SHAKE. Foaming of the solution on reconstitution is not unusual.
  3. Allow the reconstituted solution to stand for 5 minutes. Visually inspect the reconstituted solution for particulate matter and discoloration. The reconstituted solution should be colorless to light yellow and opalescent, and the solution may develop a few translucent particles as infliximab-dyyb is a protein. Do not use if the lyophilized powder has not fully dissolved or if opaque particles, discoloration, or other foreign particles are present. Do not store unused reconstituted INFLECTRA solution.
3. Dilute the total volume of the reconstituted INFLECTRA solution to 250 mL [For volumes greater than 250 mL, either use a larger infusion bag (e.g. 500 mL) or multiple 250 mL infusion bags to ensure that the concentration of the infusion solution does not exceed 4 mg/mL.] with sterile 0.9% Sodium Chloride Injection, USP, (do not dilute with any other diluent) as follows:
  1. Withdraw a volume from the 0.9% Sodium Chloride Injection, USP, 250 mL bottle or bag equal to the total volume of reconstituted INFLECTRA required for a dose. Slowly add the total volume of reconstituted INFLECTRA solution from the vial(s) to the 250 mL infusion bottle or bag.
  2. Discard any unused portion of the reconstituted INFLECTRA solution remaining in the vial(s).
  3. Gently invert the bag to mix the solution. The resulting infusion concentration should range between 0.4 mg/mL (minimum recommended concentration) and 4 mg/mL (maximum recommended concentration) of infliximab-dyyb.
4. The INFLECTRA infusion should begin within 3 hours of reconstitution and dilution. The infusion must be administered intravenously for at least 2 hours with an infusion set with an in-line, sterile, non-pyrogenic, low-protein-binding filter (pore size of 1.2 µm or less).
5. Given that the vials do not contain antibacterial preservatives, discard any unused portion of the infusion solution (do not store for reuse).

No physical biochemical compatibility studies have been conducted to evaluate the co-administration of INFLECTRA with other agents. INFLECTRA should not be infused concomitantly in the same intravenous line with other agents.

3 DOSAGE FORMS AND STRENGTHS

For injection: 100 mg of infliximab-dyyb as a white lyophilized powder in a single-dose vial for reconstitution and dilution.

4 CONTRAINDICATIONS

The use of INFLECTRA at doses >5 mg/kg is contraindicated in patients with moderate or severe heart failure [see Warnings and Precautions (5.5) and Adverse Reactions (6.1)].

INFLECTRA is contraindicated in patients with a previous severe hypersensitivity reaction to infliximab products or any of the inactive ingredients of INFLECTRA or any murine proteins [severe hypersensitivity reactions have included anaphylaxis, hypotension, and serum sickness] [see Warnings and Precautions (5.7) and Adverse Reactions (6.1)].

5 WARNINGS AND PRECAUTIONS

5.1 Serious Infections

Patients treated with infliximab products are at increased risk for developing serious infections involving various organ systems and sites that may lead to hospitalization or death.

Opportunistic infections due to bacterial, mycobacterial, invasive fungal, viral, or parasitic organisms including aspergillosis, blastomycosis, candidiasis, coccidioidomycosis, cryptococcosis, histoplasmosis, legionellosis, listeriosis, pneumocystosis, salmonellosis and tuberculosis have been reported with TNF blockers. Patients have frequently presented with disseminated rather than localized disease.

Treatment with INFLECTRA should not be initiated in patients with an active infection, including clinically important localized infections. Patients greater than 65 years of age, patients with comorbid conditions and/or patients taking concomitant immunosuppressants such as corticosteroids or methotrexate may be at greater risk of infection. The risks and benefits of treatment should be considered prior to initiating therapy in patients:

- with chronic or recurrent infection;
- who have been exposed to tuberculosis;
- with a history of an opportunistic infection;
- who have resided or traveled in areas of endemic tuberculosis or endemic mycoses, such as histoplasmosis, coccidioidomycosis, or blastomycosis; or
- with underlying conditions that may predispose them to infection.

Tuberculosis

Cases of reactivation of tuberculosis or new tuberculosis infections have been observed in patients receiving infliximab products, including patients who have previously received treatment for latent or active tuberculosis. Cases of active tuberculosis have also occurred in patients being treated with infliximab products during treatment for latent tuberculosis.

Patients should be evaluated for tuberculosis risk factors and tested for latent infection prior to initiating INFLECTRA and periodically during therapy. Treatment of latent tuberculosis infection prior to therapy with TNF blockers has been shown to reduce the risk of tuberculosis reactivation during therapy. Induration of 5 mm or greater with tuberculin skin testing should be considered a positive test result when assessing if treatment for latent tuberculosis is needed prior to initiating INFLECTRA, even for patients previously vaccinated with Bacille Calmette-Guérin (BCG).

Anti-tuberculosis therapy should also be considered prior to initiation of INFLECTRA in patients with a past history of latent or active tuberculosis in whom an adequate course of treatment cannot be confirmed, and for patients with a negative test for latent tuberculosis but having risk factors for tuberculosis infection. Consultation with a physician with expertise in the treatment of tuberculosis is recommended to aid in the decision whether initiating anti-tuberculosis therapy is appropriate for an individual patient.

Tuberculosis should be strongly considered in patients who develop a new infection during INFLECTRA treatment, especially in patients who have previously or recently traveled to countries with a high prevalence of tuberculosis, or who have had close contact with a person with active tuberculosis.

Monitoring

Patients should be closely monitored for the development of signs and symptoms of infection during and after treatment with INFLECTRA, including the development of tuberculosis in patients who tested negative for latent tuberculosis infection prior to initiating therapy. Tests for latent tuberculosis infection may also be falsely negative while on therapy with INFLECTRA.

INFLECTRA should be discontinued if a patient develops a serious infection or sepsis. A patient who develops a new infection during treatment with INFLECTRA should be closely monitored, undergo a prompt and complete diagnostic workup appropriate for an immunocompromised patient, and appropriate antimicrobial therapy should be initiated.

Invasive Fungal Infections

For patients who reside or travel in regions where mycoses are endemic, invasive fungal infection should be suspected if they develop a serious systemic illness. Appropriate empiric antifungal therapy should be considered while a diagnostic workup is being performed. Antigen and antibody testing for histoplasmosis may be negative in some patients with active infection. When feasible, the decision to administer empiric antifungal therapy in these patients should be made in consultation with a physician with expertise in the diagnosis and treatment of invasive fungal infections and should take into account both the risk for severe fungal infection and the risks of antifungal therapy.

5.2 Malignancies

Malignancies, some fatal, have been reported among children, adolescents and young adults who received treatment with TNF blockers (initiation of therapy ≤18 years of age), including infliximab products. Approximately half of these cases were lymphomas, including Hodgkin's and non-Hodgkin's lymphoma. The other cases represented a variety of malignancies, including rare malignancies that are usually associated with immunosuppression and malignancies that are not usually observed in children and adolescents. The malignancies occurred after a median of 30 months (range 1 to 84 months) after the first dose of TNF blocker therapy. Most of the patients were receiving concomitant immunosuppressants. These cases were reported postmarketing and are derived from a variety of sources, including registries and spontaneous postmarketing reports.

Lymphomas

In the controlled portions of clinical trials of all the TNF blockers, more cases of lymphoma have been observed among patients receiving a TNF blocker compared with control patients. In the controlled and open-label portions of infliximab clinical trials, 5 patients developed lymphomas among 5707 patients treated with infliximab (median duration of follow-up 1.0 years) vs. 0 lymphomas in 1600 control patients (median duration of follow-up 0.4 years). In RA patients, 2 lymphomas were observed for a rate of 0.08 cases per 100 patient-years of follow-up, which is approximately three-fold higher than expected in the general population. In the combined clinical trial population for RA, CD, PsA, AS, UC, and Ps, 5 lymphomas were observed for a rate of 0.10 cases per 100 patient-years of follow-up, which is approximately four-fold higher than expected in the general population. Patients with CD, RA or Ps, particularly patients with highly active disease and/or chronic exposure to immunosuppressant therapies, may be at a higher risk (up to several fold) than the general population for the development of lymphoma, even in the absence of TNF blockers. Cases of acute and chronic leukemia have been reported with postmarketing TNF blocker use in RA and other diseases. Even in the absence of TNF blocker therapy, patients with RA may be at a higher risk (approximately 2-fold) than the general population for the development of leukemia.

Hepatosplenic T-cell Lymphoma (HSTCL)

Postmarketing cases of hepatosplenic T-cell lymphoma (HSTCL), a rare type of T-cell lymphoma, have been reported in patients treated with TNF blockers, including infliximab products. These cases have had a very aggressive disease course and have been fatal. Almost all patients had received treatment with the immunosuppressants azathioprine or 6-mercaptopurine concomitantly with a TNF blocker at or prior to diagnosis. The majority of reported cases have occurred in patients with CD or UC and most were in adolescent and young adult males. It is uncertain whether the occurrence of HSTCL is related to TNF blockers or TNF blockers in combination with these other immunosuppressants. When treating patients, consideration of whether to use INFLECTRA alone or in combination with other immunosuppressants such as azathioprine or 6-mercaptopurine should take into account a possibility that there is a higher risk of HSTCL with combination therapy versus an observed increased risk of immunogenicity and hypersensitivity reactions with infliximab product monotherapy from the clinical trial data from studies with infliximab [see Warnings and Precautions (5.7) and Adverse Reactions (6.1)].

Skin Cancer

Melanoma and Merkel cell carcinoma have been reported in patients treated with TNF blocker therapy, including infliximab products [see Adverse Reactions (6.3)]. Periodic skin examination is recommended for all patients, particularly those with risk factors for skin cancer.

Cervical Cancer

A population-based retrospective cohort study using data from Swedish national health registries found a 2 to 3 fold increase in the incidence of invasive cervical cancer in women with RA treated with infliximab compared to biologics-naïve patients or the general population, particularly those over 60 years of age. A causal relationship between infliximab products and cervical cancer cannot be excluded. Periodic screening should continue in women treated with INFLECTRA [see Adverse Reactions (6.3)].

Other Malignancies

In the controlled portions of clinical trials of some TNF blockers, including infliximab products, more malignancies (excluding lymphoma and nonmelanoma skin cancer [NMSC]) have been observed in patients receiving those TNF blockers compared with control patients. During the controlled portions of trials with infliximab, in patients with moderately to severely active RA, CD, PsA, AS, UC and Ps, 14 patients were diagnosed with malignancies (excluding lymphoma and NMSC) among 4019 infliximab-treated patients vs. 1 among 1597 control patients (at a rate of 0.52/100 patient-years among infliximab-treated patients vs. a rate of 0.11/100 patient-years among control patients), with median duration of follow-up 0.5 years for infliximab-treated patients and 0.4 years for control patients. Of these, the most common malignancies were breast, colorectal, and melanoma. The rate of malignancies among infliximab-treated patients was similar to that expected in the general population whereas the rate in control patients was lower than expected.

In a clinical trial exploring the use of infliximab in patients with moderate to severe chronic obstructive pulmonary disease (COPD), more malignancies, the majority of lung or head and neck origin, were reported in infliximab-treated patients compared with control patients. All patients had a history of heavy smoking [see Adverse Reactions (6.1)]. Prescribers should exercise caution when considering the use of INFLECTRA in patients with moderate to severe COPD.

Ps patients should be monitored for nonmelanoma skin cancers (NMSCs), particularly those patients who have had prior prolonged phototherapy treatment. In the maintenance portion of clinical trials for infliximab, NMSCs were more common in patients with previous phototherapy [see Adverse Reactions (6.1)].

The potential role of TNF blockers in the development of malignancies is not known [see Adverse Reactions (6.1)]. Rates in clinical trials for infliximab cannot be compared to rates in clinical trials of other TNF blockers and may not predict rates observed in a broader patient population. Caution should be exercised in considering INFLECTRA treatment in patients with a history of malignancy or in continuing treatment in patients who develop malignancy while receiving INFLECTRA.

5.3 Hepatitis B Virus Reactivation

Use of TNF blockers, including infliximab products, has been associated with reactivation of hepatitis B virus (HBV) in patients who are chronic carriers of this virus. In some instances, HBV reactivation occurring in conjunction with TNF blocker therapy has been fatal. The majority of these reports have occurred in patients concomitantly receiving other medications that suppress the immune system, which may also contribute to HBV reactivation. Patients should be tested for HBV infection before initiating TNF blocker therapy, including INFLECTRA. For patients who test positive for hepatitis B surface antigen, consultation with a physician with expertise in the treatment of hepatitis B is recommended. Adequate data are not available on the safety or efficacy of treating patients who are carriers of HBV with anti-viral therapy in conjunction with TNF blocker therapy to prevent HBV reactivation. Patients who are carriers of HBV and require treatment with TNF blockers should be closely monitored for clinical and laboratory signs of active HBV infection throughout therapy and for several months following termination of therapy. In patients who develop HBV reactivation, TNF blockers should be stopped and antiviral therapy with appropriate supportive treatment should be initiated. The safety of resuming TNF blocker therapy after HBV reactivation is controlled is not known. Therefore, prescribers should exercise caution when considering resumption of TNF blocker therapy in this situation and monitor patients closely.

5.4 Hepatotoxicity

Severe hepatic reactions, including acute liver failure, jaundice, hepatitis and cholestasis, have been reported in postmarketing data in patients receiving infliximab products. Autoimmune hepatitis has been diagnosed in some of these cases. Severe hepatic reactions occurred between 2 weeks to more than 1 year after initiation of infliximab products; elevations in hepatic aminotransferase levels were not noted prior to discovery of the liver injury in many of these cases. Some of these cases were fatal or necessitated liver transplantation. Patients with symptoms or signs of liver dysfunction should be evaluated for evidence of liver injury. If jaundice and/or marked liver enzyme elevations (e.g., ≥5 times the upper limit of normal) develop, INFLECTRA should be discontinued, and a thorough investigation of the abnormality should be undertaken. In clinical trials, mild or moderate elevations of ALT and AST have been observed in patients receiving infliximab products without progression to severe hepatic injury [see Adverse Reactions (6.1)].

5.5 Heart Failure

The use of INFLECTRA at doses > 5 mg/kg is contraindicated in patients with moderate or severe heart failure. A randomized, double-blind, placebo-controlled study evaluated the use of infliximab (5 mg/kg or 10 mg/kg at Weeks 0, 2 and 6) in patients with moderate or severe heart failure [New York Heart Association (NYHA) Functional Class III/IV]. Compared to patients who received placebo, there was a higher rate of mortality and a higher risk of hospitalization at Week 28 due to heart failure in patients who received the 10 mg/kg infliximab dose, and higher rates of cardiovascular adverse events in patients who received infliximab doses of 5 mg/kg and 10 mg/kg.

There have been postmarketing reports of new onset and worsening heart failure, with and without identifiable precipitating factors (e.g., pre-existing cardiovascular disease), in patients treated with infliximab products. Some of these patients have been under 50 years of age.

If a decision is made to administer INFLECTRA (≤ 5 mg/kg) to patients with moderate or severe heart failure or to administer INFLECTRA (any approved dose) to patients with mild heart failure, they should be closely monitored during therapy, and INFLECTRA should be discontinued if new or worsening symptoms of heart failure appear [see Contraindications (4) and Adverse Reactions (6.1)].

5.6 Hematologic Reactions

Cases of leukopenia, neutropenia, thrombocytopenia, and pancytopenia, some with a fatal outcome, have been reported in patients receiving infliximab products. The causal relationship to infliximab product therapy remains unclear. Although no high-risk group(s) has been identified, caution should be exercised in patients being treated with INFLECTRA who have ongoing or a history of significant hematologic abnormalities. All patients should be advised to seek immediate medical attention if they develop signs and symptoms suggestive of blood dyscrasias or infection (e.g., persistent fever) while on INFLECTRA. Discontinuation of INFLECTRA therapy should be considered in patients who develop significant hematologic abnormalities.

5.7 Hypersensitivity

Infliximab products have been associated with hypersensitivity reactions that vary in their time of onset and required hospitalization in some cases. Most hypersensitivity reactions (including anaphylaxis, urticaria, dyspnea, and/or hypotension), have occurred during or within 2 hours of infliximab product infusion.

However, in some cases, serum sickness-like reactions have been observed in patients after initial therapy with infliximab products (i.e., as early as after the second dose), and when therapy with infliximab products was reinstituted following an extended period without treatment. Symptoms associated with these reactions include fever, rash, headache, sore throat, myalgias, polyarthralgias, hand and facial edema and/or dysphagia. These reactions were associated with a marked increase in antibodies to infliximab products, loss of detectable serum concentrations of infliximab products, and possible loss of drug efficacy.

INFLECTRA should be discontinued for severe hypersensitivity reactions. Medications for the treatment of hypersensitivity reactions (e.g., acetaminophen, antihistamines, corticosteroids and/or epinephrine) should be available for immediate use in the event of a reaction [see Dosage and Administration (2.10) and Adverse Reactions (6.1)].

In RA, CD and Ps clinical trials, re-administration of infliximab after a period of no treatment resulted in a higher incidence of infusion reactions relative to regular maintenance treatment [see Adverse Reactions (6.1)]. In general, the benefit-risk of readministration of INFLECTRA after a period of no-treatment, especially as a re-induction regimen given at weeks 0, 2 and 6, should be carefully considered. In the case where INFLECTRA maintenance therapy for Ps is interrupted, INFLECTRA should be reinitiated as a single dose followed by maintenance therapy.

5.8 Cardiovascular and Cerebrovascular Reactions During and After Infusion

Serious cerebrovascular accidents, myocardial ischemia/infarction (some fatal), hypotension, hypertension, and arrhythmias have been reported during and within 24 hours of initiation of infliximab product infusion. Cases of transient visual loss have been reported during or within 2 hours of infliximab product infusion. Monitor patients during infusion and if serious reaction occurs, discontinue infusion. Further management of reactions should be dictated by signs and symptoms [see Adverse Reactions (6)].

5.9 Neurologic Reactions

Infliximab products and agents that inhibit TNF have been associated with CNS manifestation of systemic vasculitis, seizure and new onset or exacerbation of clinical symptoms and/or radiographic evidence of central nervous system demyelinating disorders, including multiple sclerosis and optic neuritis, and peripheral demyelinating disorders, including Guillain-Barré syndrome. Prescribers should exercise caution in considering the use of INFLECTRA in patients with these neurologic disorders and should consider discontinuation of INFLECTRA if these disorders develop.

5.10 Concurrent Administration with Other Biological Products

Serious infections and neutropenia were seen in clinical studies with concurrent use of anakinra and another TNF blocker, etanercept, with no added clinical benefit compared to etanercept alone. Because of the nature of the adverse reactions seen with the concurrent use of etanercept and anakinra therapy, similar toxicities may also result from the concurrent use of anakinra and other TNF blockers. Therefore, the concurrent use of INFLECTRA and anakinra is not recommended.

In clinical studies, concurrent administration of TNF blockers and abatacept have been associated with an increased risk of infections including serious infections compared with TNF blockers alone, without increased clinical benefit. Therefore, the concurrent use of INFLECTRA and abatacept is not recommended [see Drug Interactions (7.1)].

There is insufficient information regarding the concurrent use of infliximab products with other biological products used to treat the same conditions as INFLECTRA. The concurrent use of INFLECTRA with these biological products is not recommended because of the possibility of an increased risk of infection [see Drug Interactions (7.1)].

5.11 Switching Between Biological Disease-Modifying Antirheumatic Drugs (DMARDs)

Care should be taken when switching from one biologic to another, since overlapping biological activity may further increase the risk of infection.

5.12 Autoimmunity

Treatment with infliximab products may result in the formation of autoantibodies and in the development of a lupus-like syndrome. If a patient develops symptoms suggestive of a lupus-like syndrome following treatment with INFLECTRA, treatment should be discontinued [see Adverse Reactions (6.1)].

5.13 Vaccinations and Use of Live Vaccines/Therapeutic Infectious Agents

Vaccinations

Prior to initiating INFLECTRA in pediatric and adult patients, update vaccinations in accordance with current vaccination guidelines.

Live Vaccines and Therapeutic Infectious Agents

In patients receiving TNF blockers, limited data are available on the response to vaccination with live vaccines or on the secondary transmission of infection by live vaccines. Use of live vaccines can result in clinical infections, including disseminated infections. The concurrent administration of live vaccines with INFLECTRA is not recommended.

Fatal outcome due to disseminated BCG infection has been reported in an infant who received a BCG vaccine after in utero exposure to infliximab products. Infliximab products are known to cross the placenta and have been detected up to 6 months following birth. At least a six month waiting period following birth is recommended before the administration of any live vaccine to infants exposed in utero to infliximab products.

Other uses of therapeutic infectious agents such as live attenuated bacteria (e.g., BCG bladder instillation for the treatment of cancer) could result in clinical infections, including disseminated infections. It is recommended that therapeutic infectious agents not be given concurrently with INFLECTRA.

6 ADVERSE REACTIONS

6.1 Clinical Trials Experience

Because clinical trials are conducted under widely varying conditions, adverse reaction rates observed in the clinical trials of a drug cannot be directly compared to rates in the clinical trials of another drug and may not reflect the rates observed in practice.

Adverse Reactions in Adults

The data described herein reflect exposure to infliximab in 4779 adult patients (1304 patients with RA, 1106 patients with CD, 202 with AS, 293 with PsA, 484 with UC, 1373 with Ps, and 17 patients with other conditions), including 2625 patients exposed beyond 30 weeks and 374 exposed beyond 1 year. [For information on adverse reactions in pediatric patients see Adverse Reactions (6.1)]. One of the most common reasons for discontinuation of treatment was infusion-related reactions (e.g., dyspnea, flushing, headache and rash).

Infusion-Related Reactions

Adverse Reactions During or Shortly After Infusion

An infusion reaction was defined in clinical trials as any adverse event occurring during an infusion or within 1 hour after an infusion. In all the clinical studies, approximately 20% of infliximab-treated patients experienced an infusion reaction compared with 10% of placebo-treated patients. Of infliximab-treated patients who had an infusion reaction during the induction period, 27% experienced an infusion reaction during the maintenance period. Of patients who did not have an infusion reaction during the induction period, 9% experienced an infusion reaction during the maintenance period.

Among all infliximab infusions, 3% were accompanied by nonspecific symptoms such as fever or chills, 1% were accompanied by cardiopulmonary reactions (primarily chest pain, hypotension, hypertension or dyspnea), and <1% were accompanied by pruritus, urticaria, or the combined symptoms of pruritus/urticaria and cardiopulmonary reactions. Serious infusion reactions occurred in <1% of patients and included anaphylaxis, convulsions, erythematous rash and hypotension. Approximately 3% of patients discontinued treatment with infliximab because of infusion reactions, and all patients recovered with treatment and/or discontinuation of the infusion. Infliximab infusions beyond the initial infusion were not associated with a higher incidence of reactions. The infusion reaction rates remained stable in Ps through 1 year in Ps Study I. In psoriasis Study II, the rates were variable over time and somewhat higher following the final infusion than after the initial infusion. Across the 3 Ps studies, the percent of total infusions resulting in infusion reactions (i.e., an adverse event occurring within 1 hour) was 7% in the 3 mg/kg group, 4% in the 5 mg/kg group, and 1% in the placebo group.

Patients who became positive for antibodies to infliximab were more likely (approximately two to three-fold) to have an infusion reaction than were those who were negative. Use of concomitant immunosuppressant agents appeared to reduce the frequency of both antibodies to infliximab and infusion reactions [see Adverse Reactions (6.2) and Drug Interactions (7.3)].

Infusion Reactions Following Re-administration

In a clinical trial of patients with moderate to severe Ps designed to assess the efficacy of long-term maintenance therapy versus re-treatment with an induction regimen of infliximab following disease flare, 4% (8/219) of patients in the re-treatment induction therapy arm experienced serious infusion reactions versus <1% (1/222) in the maintenance therapy arm. Patients enrolled in this trial did not receive any concomitant immunosuppressant therapy. In this study, the majority of serious infusion reactions occurred during the second infusion at Week 2. Symptoms included, but were not limited to, dyspnea, urticaria, facial edema, and hypotension. In all cases, treatment with infliximab was discontinued and/or other treatment instituted with complete resolution of signs and symptoms.

Delayed Reactions/Reactions Following Re-administration

In Ps studies, approximately 1% of patients treated with infliximab experienced a possible delayed hypersensitivity reaction, generally reported as serum sickness or a combination of arthralgia and/or myalgia with fever and/or rash. These reactions generally occurred within 2 weeks after repeat infusion.

Infections

In infliximab clinical studies, treated infections were reported in 36% of patients treated with infliximab (average of 51 weeks of follow-up) and in 25% of placebo-treated patients (average of 37 weeks of follow-up). The infections most frequently reported were respiratory tract infections (including sinusitis, pharyngitis, and bronchitis) and urinary tract infections. Among patients treated with infliximab, serious infections included pneumonia, cellulitis, abscess, skin ulceration, sepsis, and bacterial infection. In clinical trials, 7 opportunistic infections were reported; 2 cases each of coccidioidomycosis (1 case was fatal) and histoplasmosis (1 case was fatal), and 1 case each of pneumocystosis, nocardiosis and cytomegalovirus. Tuberculosis (TB) was reported in 14 patients, 4 of whom died due to miliary tuberculosis. Other cases of TB, including disseminated TB, also have been reported postmarketing. Most of these cases of TB occurred within the first 2 months after initiation of therapy with infliximab and may reflect recrudescence of latent disease [see Warnings and Precautions (5.1)]. In the 1-year placebo-controlled studies RA I and RA II, 5.3% of patients receiving infliximab every 8 weeks with MTX developed serious infections as compared to 3.4% of placebo patients receiving MTX. Of 924 patients receiving infliximab, 1.7% developed pneumonia and 0.4% developed TB, when compared to 0.3% and 0.0% in the placebo arm respectively. In a shorter (22-week) placebo-controlled study of 1082 RA patients randomized to receive placebo, 3 mg/kg or 10 mg/kg infusions with infliximab at 0, 2, and 6 weeks, followed by every 8 weeks with MTX, serious infections were more frequent in the 10 mg/kg infliximab group (5.3%) than the 3 mg/kg or placebo groups (1.7% in both). During the 54-week Crohn's II Study, 15% of patients with fistulizing CD developed a new fistula-related abscess.

In clinical studies with infliximab in patients with UC, infections treated with antimicrobials were reported in 27% of patients treated with infliximab (average of 41 weeks of follow-up) and in 18% of placebo-treated patients (average 32 weeks of follow-up). The types of infections, including serious infections, reported in patients with UC were similar to those reported in other clinical studies.

The onset of serious infections may be preceded by constitutional symptoms such as fever, chills, weight loss, and fatigue. The majority of serious infections, however, may also be preceded by signs or symptoms localized to the site of the infection.

Autoantibodies/Lupus-like Syndrome

Approximately half of patients treated with infliximab in clinical trials who were antinuclear antibody (ANA) negative at baseline developed a positive ANA during the trial compared with approximately one-fifth of placebo-treated patients. Anti-dsDNA antibodies were newly detected in approximately one-fifth of patients treated with infliximab compared with 0% of placebo-treated patients. Reports of lupus and lupus-like syndromes, however, remain uncommon.

Malignancies

In controlled trials, more patients treated with infliximab developed malignancies than placebo-treated patients [see Warnings and Precautions (5.2)].

In a randomized controlled clinical trial exploring the use of infliximab in patients with moderate to severe COPD who were either current smokers or ex-smokers, 157 patients were treated with infliximab at doses similar to those used in RA and CD. Of these infliximab-treated patients, 9 developed a malignancy, including 1 lymphoma, for a rate of 7.67 cases per 100 patient-years of follow-up (median duration of follow-up 0.8 years; 95% CI 3.51 – 14.56). There was 1 reported malignancy among 77 control patients for a rate of 1.63 cases per 100 patient-years of follow-up (median duration of follow-up 0.8 years; 95% CI 0.04 – 9.10). The majority of the malignancies developed in the lung or head and neck [see Warnings and Precautions (5.2)].

Adverse Reactions in Patients with NYHA Class III/IV Heart Failure

In a randomized, double-blind study evaluating infliximab in moderate or severe heart failure (NYHA Class III/IV; left ventricular ejection fraction ≤35%), 150 patients were randomized to receive treatment with 3 infusions of infliximab at 10 mg/kg, 5 mg/kg, or placebo, at 0, 2, and 6 weeks. Higher incidences of mortality and hospitalization due to worsening heart failure were observed in patients receiving the 10 mg/kg infliximab dose. At 1 year, 8 patients in the 10 mg/kg infliximab group had died compared with 4 deaths each in the 5 mg/kg infliximab and the placebo groups. There were trends toward increased dyspnea, hypotension, angina, and dizziness in both the 10 mg/kg and 5 mg/kg infliximab treatment groups, versus placebo. Infliximab products have not been studied in patients with mild heart failure (NYHA Class I/II) [see Contraindications (4) and Warnings and Precautions (5.5)].

Hepatotoxicity

Severe liver injury, including acute liver failure and autoimmune hepatitis, has been reported in patients receiving infliximab products [see Warnings and Precautions (5.4)]. Reactivation of hepatitis B virus has occurred in patients receiving TNF blockers, including infliximab products, who are chronic carriers of this virus [see Warnings and Precautions (5.3)].

In clinical trials in RA, CD, UC, AS, Ps, and PsA, elevations of aminotransferases were observed (ALT more common than AST) in a greater proportion of patients receiving infliximab than in controls (Table 1), both when infliximab was given as monotherapy and when it was used in combination with other immunosuppressive agents. In general, patients who developed ALT and AST elevations were asymptomatic, and the abnormalities decreased or resolved with either continuation or discontinuation of infliximab, or modification of concomitant medications.

Table 1 Proportion of Patients with Elevated ALT in Clinical Trials in Adults
 | Proportion of patients with elevated ALT
 | >1 to 3 × ULN |  | ≥3 × ULN |  | ≥5 × ULN
 | Placebo | Infliximab | Placebo | Infliximab | Placebo | Infliximab
Rheumatoid arthritis [Placebo patients received methotrexate while patients treated with infliximab received both infliximab and methotrexate. Median follow-up was 58 weeks.] | 24% | 34% | 3% | 4% | <1% | <1%
Crohn's disease [Placebo patients in the 2 Phase 3 trials in CD received an initial dose of 5 mg/kg infliximab at study start and were on placebo in the maintenance phase. Patients who were randomized to the placebo maintenance group and then later crossed over to infliximab are included in the infliximab group in ALT analysis. Median follow-up was 54 weeks.] | 34% | 39% | 4% | 5% | 0% | 2%
Ulcerative colitis [Median follow-up was 30 weeks. Specifically, the median duration of follow-up was 30 weeks for placebo and 31 weeks for infliximab.] | 12% | 17% | 1% | 2% | <1% | <1%
Ankylosing spondylitis [Median follow-up was 24 weeks for the placebo group and 102 weeks for infliximab group.] | 15% | 51% | 0% | 10% | 0% | 4%
Psoriatic arthritis [Median follow-up was 39 weeks for infliximab group and 18 weeks for the placebo group.] | 16% | 50% | 0% | 7% | 0% | 2%
Plaque psoriasis [ALT values are obtained in 2 Phase 3 Ps studies with median follow-up of 50 weeks for infliximab and 16 weeks for placebo.] | 24% | 49% | <1% | 8% | 0% | 3%

Adverse Reactions in Psoriasis Studies

During the placebo-controlled portion across the 3 clinical trials up to week 16, the proportion of patients who experienced at least 1 serious adverse reaction (SAE; defined as resulting in death, life threatening, requires hospitalization, or persistent or significant disability/incapacity) was 0.5% in the 3 mg/kg infliximab group, 1.9% in the placebo group, and 1.6% in the 5 mg/kg infliximab group.

Among patients in the 2 Phase 3 studies, 12.4% of patients receiving infliximab 5 mg/kg every 8 weeks through 1 year of maintenance treatment experienced at least 1 SAE in Study I. In Study II, 4.1% and 4.7% of patients receiving infliximab 3 mg/kg and 5 mg/kg every 8 weeks, respectively, through 1 year of maintenance treatment experienced at least 1 SAE.

One death due to bacterial sepsis occurred 25 days after the second infusion of 5 mg/kg of infliximab. Serious infections included sepsis, and abscesses. In Study I, 2.7% of patients receiving infliximab 5 mg/kg every 8 weeks through 1 year of maintenance treatment experienced at least 1 serious infection. In Study II, 1.0% and 1.3% of patients receiving infliximab 3 mg/kg and 5 mg/kg, respectively, through 1 year of treatment experienced at least 1 serious infection. The most common serious infection (requiring hospitalization) was abscess (skin, throat, and peri-rectal) reported by 5 (0.7%) patients in the 5 mg/kg infliximab group. Two active cases of tuberculosis were reported: 6 weeks and 34 weeks after starting infliximab.

In the placebo-controlled portion of the Ps studies, 7 of 1123 patients who received infliximab at any dose were diagnosed with at least one NMSC compared to 0 of 334 patients who received placebo.

In the Ps studies, 1% (15/1373) of patients experienced serum sickness or a combination of arthralgia and/or myalgia with fever, and/or rash, usually early in the treatment course. Of these patients, 6 required hospitalization due to fever, severe myalgia, arthralgia, swollen joints, and immobility.

Other Adverse Reactions in Adults

Safety data are available from 4779 infliximab-treated adult patients, including 1304 with RA, 1106 with CD, 484 with UC, 202 with AS, 293 with PsA, 1373 with Ps and 17 with other conditions. [For information on other adverse reactions in pediatric patients, see Adverse Reactions (6.1)]. Adverse reactions reported in ≥5% of all patients with RA receiving 4 or more infusions are in Table 2. The types and frequencies of adverse reactions observed were similar in infliximab-treated RA, AS, PsA, Ps and CD patients except for abdominal pain, which occurred in 26% of infliximab-treated patients with CD. In the CD studies, there were insufficient numbers and duration of follow-up for patients who never received infliximab to provide meaningful comparisons.

Table 2 Adverse Reactions that Occurred in ≥ 5% of Patients who Received ≥ 4 Infliximab Infusions for RA
 | Placebo | Infliximab
 | (n=350) | (n=1129)
Average weeks of follow-up | 59 weeks | 66 weeks
Upper respiratory tract infection | 25% | 32%
Nausea | 20% | 21%
Headache | 14% | 18%
Sinusitis | 8% | 14%
Diarrhea | 12% | 12%
Abdominal pain | 8% | 12%
Pharyngitis | 8% | 12%
Coughing | 8% | 12%
Bronchitis | 9% | 10%
Rash | 5% | 10%
Dyspepsia | 7% | 10%
Fatigue | 7% | 9%
Urinary tract infection | 6% | 8%
Pain | 7% | 8%
Arthralgia | 7% | 8%
Pruritus | 2% | 7%
Fever | 4% | 7%
Hypertension | 5% | 7%
Moniliasis | 3% | 5%

The most common serious adverse reactions observed in clinical trials were infections [see Adverse Reactions (6.1)]. Other serious, medically relevant adverse reactions ≥0.2% or clinically significant adverse reactions by body system were as follows:

- Body as a whole: allergic reaction, edema
- Blood: pancytopenia
- Cardiovascular: hypotension
- Gastrointestinal: constipation, intestinal obstruction
- Central and Peripheral Nervous: dizziness
- Heart Rate and Rhythm: bradycardia
- Liver and Biliary: hepatitis
- Metabolic and Nutritional: dehydration
- Platelet, Bleeding and Clotting: thrombocytopenia
- Neoplasms: lymphoma
- Red Blood Cell: anemia, hemolytic anemia
- Resistance Mechanism: cellulitis, sepsis, serum sickness, sarcoidosis
- Respiratory: lower respiratory tract infection (including pneumonia), pleurisy, pulmonary edema
- Skin and Appendages: increased sweating
- Vascular (Extracardiac): thrombophlebitis
- White Cell and Reticuloendothelial: leukopenia, lymphadenopathy

Adverse Reactions in Pediatric Patients

Adverse Reactions in Pediatric Patients with Crohn's Disease

There were some differences in the adverse reactions observed in the pediatric patients receiving infliximab compared to those observed in adults with CD. These differences are discussed in the following paragraphs.

The following adverse reactions were reported more commonly in 103 randomized pediatric CD patients administered 5 mg/kg infliximab through 54 weeks than in 385 adult CD patients receiving a similar treatment regimen: anemia (11%), leukopenia (9%), flushing (9%), viral infection (8%), neutropenia (7%), bone fracture (7%), bacterial infection (6%), and respiratory tract allergic reaction (6%).

Infections were reported in 56% of randomized pediatric patients in Study Peds Crohn's and in 50% of adult patients in Study Crohn's I. In Study Peds Crohn's, infections were reported more frequently for patients who received every 8-week as opposed to every 12-week infusions (74% and 38%, respectively), while serious infections were reported for 3 patients in the every 8-week and 4 patients in the every 12-week maintenance treatment group. The most commonly reported infections were upper respiratory tract infection and pharyngitis, and the most commonly reported serious infection was abscess. Pneumonia was reported for 3 patients, (2 in the every 8- week and 1 in the every 12-week maintenance treatment groups). Herpes zoster was reported for 2 patients in the every 8-week maintenance treatment group.

In Study Peds Crohn's, 18% of randomized patients experienced 1 or more infusion reactions, with no notable difference between treatment groups. Of the 112 patients in Study Peds Crohn's, there were no serious infusion reactions, and 2 patients had non-serious anaphylactoid reactions.

Elevations of ALT up to 3 times the upper limit of normal (ULN) were seen in 18% of pediatric patients in CD clinical trials; 4% had ALT elevations ≥3 × ULN, and 1% had elevations ≥5 × ULN. (Median follow-up was 53 weeks).

Adverse Reactions in Pediatric Patients with Ulcerative Colitis

Overall, the adverse reactions reported in the pediatric UC trial and adult UC (Study UC I and Study UC II) studies were generally consistent. In a pediatric UC trial, the most common adverse reactions were upper respiratory tract infection, pharyngitis, abdominal pain, fever, and headache.

Infections were reported in 31 (52%) of 60 treated patients in the pediatric UC trial and 22 (37%) required oral or parenteral antimicrobial treatment. The proportion of patients with infections in the pediatric UC trial was similar to that in the pediatric CD study (Study Peds Crohn's) but higher than the proportion in the adults' UC studies (Study UC I and Study UC II). The overall incidence of infections in the pediatric UC trial was 13/22 (59%) in the every 8 week maintenance treatment group. Upper respiratory tract infection (7/60 [12%]) and pharyngitis (5/60 [8%]) were the most frequently reported respiratory system infections. Serious infections were reported in 12% (7/60) of all treated patients.

Elevations of ALT up to 3 times the upper limit of normal (ULN) were seen in 17% (10/60) of pediatric patients in the pediatric UC trial; 7% (4/60) had ALT elevations ≥3 × ULN, and 2% (1/60) had elevations ≥5 × ULN (median follow-up was 49 weeks).

Overall, 8 of 60 (13%) treated patients experienced one or more infusion reactions, including 4 of 22 (18%) patients in the every 8-week treatment maintenance group. No serious infusion reactions were reported.

In the pediatric UC trial, 45 patients were in the 12 to 17 year age group and 15 in the 6 to 11 year age group. The numbers of patients in each subgroup are too small to make any definitive conclusions about the effect of age on safety events. There were higher proportions of patients with serious adverse events (40% vs. 18%) and discontinuation due to adverse events (40% vs. 16%) in the younger age group than in the older age group. While the proportion of patients with infections was also higher in the younger age group (60% vs. 49%), for serious infections, the proportions were similar in the two age groups (13% in the 6 to 11 year age group vs. 11% in the 12 to 17 year age group). Overall proportions of adverse reactions, including infusion reactions, were similar between the 6 to 11 and 12 to 17 year age groups (13%).

6.2 Immunogenicity

As with all therapeutic proteins, there is potential for immunogenicity. The detection of antibody formation is highly dependent on the sensitivity and specificity of the assay. Additionally, the observed incidence of antibody (including neutralizing antibody) positivity in an assay may be influenced by several factors, including assay methodology, sample handling, timing of sample collection, concomitant medications, and underlying disease. For these reasons, comparison of the incidence of antibodies in the studies described below with the incidence of antibodies in other studies or to other infliximab products may be misleading.

Treatment with infliximab products can be associated with the development of antibodies to infliximab products. An enzyme immunoassay (EIA) method was originally used to measure anti-infliximab antibodies in clinical studies of infliximab. The EIA method is subject to interference by serum infliximab, possibly resulting in an underestimation of the rate of patient antibody formation. A separate, drug-tolerant electrochemiluminescence immunoassay (ECLIA) method for detecting antibodies to infliximab was subsequently developed and validated. This method is 60-fold more sensitive than the original EIA. With the ECLIA method, all clinical samples can be classified as either positive or negative for antibodies to infliximab without the need for the inconclusive category.

The incidence of antibodies to infliximab was based on the original EIA method in all clinical studies of infliximab except for the Phase 3 study in pediatric patients with UC where the incidence of antibodies to infliximab was detected using both the EIA and ECLIA methods.

Immunogenicity in Adult Patients

The incidence of antibodies to infliximab in patients with RA and CD given a 3-dose induction regimen followed by maintenance dosing was approximately 10% as assessed through 1 to 2 years of infliximab treatment. A higher incidence of antibodies to infliximab was observed in CD patients receiving infliximab after drug-free intervals >16 weeks. In a PsA study in which 191 patients received 5 mg/kg with or without MTX, antibodies to infliximab occurred in 15% of patients. The majority of antibody-positive patients had low titers. Antibody development was lower among RA and CD patients receiving immunosuppressant therapies such as 6-MP/AZA or MTX. Patients who were antibody-positive were more likely to have higher rates of clearance, have reduced efficacy, and to experience an infusion reaction than were patients who were antibody negative [see Adverse Reactions (6.1)]. In the Ps Study II, which included both the 5 mg/kg and 3 mg/kg doses, antibodies were observed in 36% of patients treated with 5 mg/kg every 8 weeks for 1 year, and in 51% of patients treated with 3 mg/kg every 8 weeks for 1 year.

In the Ps Study III, which also included both the 5 mg/kg and 3 mg/kg doses, antibodies were observed in 20% of patients treated with 5 mg/kg induction (weeks 0, 2 and 6), and in 27% of patients treated with 3 mg/kg induction. Despite the increase in antibody formation, the infusion reaction rates in Studies I and II in patients treated with 5 mg/kg induction followed by every 8 week maintenance for 1 year and in Study III in patients treated with 5 mg/kg induction (14.1% – 23.0%) and serious infusion reaction rates (<1%) were similar to those observed in other study populations. The clinical significance of apparent increased immunogenicity on efficacy and infusion reactions in Ps patients as compared to patients with other diseases treated with infliximab products over the long term is not known.

Immunogenicity in Pediatric Patients with Crohn's Disease

In Study Peds Crohn's, in which all patients received stable doses of 6-MP, AZA, or MTX, excluding inconclusive samples, 3 of 24 patients had antibodies to infliximab. Although 105 patients were tested for antibodies to infliximab, 81 patients were classified as inconclusive because they could not be ruled as negative due to assay interference by the presence of infliximab in the sample.

Immunogenicity in Pediatric Patients with Ulcerative Colitis

In the pediatric UC trial, 58 patients were evaluated for antibodies to infliximab using the EIA as well as the drug-tolerant ECLIA. With the EIA, 4 of 58 (7%) patients had antibodies to infliximab. With the ECLIA, 30 of 58 (52%) patients had antibodies to infliximab. The higher incidence of antibodies to infliximab by the ECLIA method was due to the 60-fold higher sensitivity compared to the EIA method. While EIA-positive patients generally had undetectable trough infliximab concentrations, ECLIA-positive patients could have detectable trough concentrations of infliximab because the ECLIA assay is more sensitive and drug-tolerant.

6.3 Postmarketing Experience

Adverse reactions, some with fatal outcomes, have been identified during post approval use of infliximab products in adult and pediatric patients. Because these reactions are reported voluntarily from a population of uncertain size, it is not always possible to reliably estimate their frequency or establish a causal relationship to drug exposure.

Postmarketing Adverse Reactions in Adults and Pediatric Patients

- Neutropenia [see Warnings and Precautions (5.6)], agranulocytosis (including infants exposed in utero to infliximab products), idiopathic thrombocytopenic purpura, thrombotic thrombocytopenic purpura.
- Interstitial lung disease (including pulmonary fibrosis/interstitial pneumonitis and rapidly progressive disease).
- Pericardial effusion, systemic and cutaneous vasculitis.
- Erythema multiforme, Stevens-Johnson Syndrome, toxic epidermal necrolysis, linear IgA bullous dermatosis (LABD), acute generalized exanthematous pustulosis (AGEP), worsening psoriasis (all subtypes including pustular, primarily palmoplantar), lichenoid reactions.
- Peripheral demyelinating disorders (such as Guillain-Barré syndrome, chronic inflammatory demyelinating polyneuropathy, and multifocal motor neuropathy) transverse myelitis, and neuropathies (additional neurologic reactions have also been observed) [see Warnings and Precautions (5.9)].
- Acute liver failure, jaundice, hepatitis, and cholestasis [see Warnings and Precautions (5.4)]
- Serious infections [see Warnings and Precautions (5.1)] and vaccine breakthrough infection including bovine tuberculosis (disseminated BCG infection) following vaccination in an infant exposed in utero to infliximab products [see Warnings and Precautions (5.13)].
- Malignancies, including leukemia, melanoma, Merkel cell carcinoma, and cervical cancer [see Warnings and Precautions (5.2)]
- Anaphylactic reactions, including anaphylactic shock, laryngeal/pharyngeal edema and severe bronchospasm, and seizure have been associated with administration of infliximab products.
- Transient visual loss have been reported in association with infliximab products during or within 2 hours of infusion. Cerebrovascular accidents, myocardial ischemia/infarction (some fatal), and arrhythmia occurring within 24 hours of initiation of infusion have also been reported [see Warnings and Precautions (5.8)].
- New onset immune disorders (e.g., psoriasis, rheumatoid arthritis, inflammatory bowel disease).

Postmarketing Serious Adverse Reactions in Pediatric Patients

The following serious adverse reactions have been reported in the postmarketing experience in pediatric patients: infections (some fatal) including opportunistic infections and tuberculosis, infusion reactions, hypersensitivity reactions, malignancies, including hepatosplenic T-cell lymphomas [see Boxed Warning and Warnings and Precautions (5.2)], transient hepatic enzyme abnormalities, lupus-like syndromes, and the development of autoantibodies.

7 DRUG INTERACTIONS

7.1 Other Biological Products

The combination of INFLECTRA with other biological products used to treat the same conditions as INFLECTRA is not recommended [see Warnings and Precautions (5.10)].

An increased risk of serious infections was seen in clinical studies of other TNF blockers used in combination with anakinra or abatacept, with no added clinical benefit. Because of the nature of the adverse reactions seen with these combinations with TNF blocker therapy, similar toxicities may also result from the combination of anakinra or abatacept with other TNF blockers. Therefore, the combination of INFLECTRA and anakinra or abatacept is not recommended [see Warnings and Precautions (5.10)].

The concomitant use of tocilizumab with biological DMARDs such as TNF antagonists, including INFLECTRA, should be avoided because of the possibility of increased immunosuppression and increased risk of infection.

7.2 Methotrexate and Other Concomitant Medications

Specific drug interaction studies, including interactions with methotrexate (MTX), have not been conducted. The majority of patients in RA or CD clinical studies received one or more concomitant medications. In RA, concomitant medications besides MTX were nonsteroidal anti-inflammatory agents (NSAIDs), folic acid, corticosteroids and/or narcotics. Concomitant CD medications were antibiotics, antivirals, corticosteroids, 6-MP/AZA and aminosalicylates. In PsA clinical trials, concomitant medications included MTX in approximately half of the patients as well as NSAIDs, folic acid and corticosteroids. Concomitant MTX use may decrease the incidence of anti-drug antibody production and increase infliximab product concentrations.

7.3 Immunosuppressants

Patients with CD who received immunosuppressants tended to experience fewer infusion reactions compared to patients on no immunosuppressants [see Adverse Reactions (6.1)]. Serum infliximab concentrations appeared to be unaffected by baseline use of medications for the treatment of CD including corticosteroids, antibiotics (metronidazole or ciprofloxacin) and aminosalicylates.

7.4 Cytochrome P450 Substrates

The formation of CYP450 enzymes may be suppressed by increased levels of cytokines (e.g., TNFα, IL-1, IL-6, IL-10, IFN) during chronic inflammation. Therefore, it is expected that for a molecule that antagonizes cytokine activity, such as infliximab products, the formation of CYP450 enzymes could be normalized. Upon initiation or discontinuation of INFLECTRA in patients being treated with CYP450 substrates with a narrow therapeutic index, monitoring of the effect (e.g., warfarin) or drug concentration (e.g., cyclosporine or theophylline) is recommended and the individual dose of the drug product may be adjusted as needed.

7.5 Live Vaccines/Therapeutic Infectious Agents

It is recommended that live vaccines not be given concurrently with INFLECTRA. It is also recommended that live vaccines not be given to infants after in utero exposure to infliximab products for at least 6 months following birth [see Warnings and Precautions (5.13)].

It is recommended that therapeutic infectious agents not be given concurrently with INFLECTRA [see Warnings and Precautions (5.13)].

8 USE IN SPECIFIC POPULATIONS

8.1 Pregnancy

Risk Summary

Available observational studies in pregnant women exposed to infliximab products showed no increased risk of major malformations among live births as compared to those exposed to non-biologics. However, findings on other birth and maternal outcomes were not consistent across studies of different study design and conduct (see Data).

Monoclonal antibodies such as infliximab products are transferred across the placenta during the third trimester of pregnancy and may affect immune response in the in utero exposed infant (see Clinical Considerations). Because infliximab products do not cross-react with TNFα in species other than humans and chimpanzees, animal reproduction studies have not been conducted with infliximab products. In a developmental study conducted in mice using an analogous antibody, no evidence of maternal toxicity or fetal harm was observed (see Data).

All pregnancies have a background risk of birth defect, loss, or other adverse outcomes.

The estimated background risk of major birth defects and miscarriage for the indicated populations is unknown. In the U.S. general population, the estimated background risk of major birth defects and miscarriage in clinically recognized pregnancies is 2–4% and 15–20%, respectively.

Clinical Considerations

Disease-Associated Maternal and/or Embryo/Fetal Risk

Published data suggest that there is an increased risk of adverse pregnancy outcomes in women with inflammatory bowel disease or rheumatoid arthritis associated with increased disease activity. Adverse pregnancy outcomes include preterm delivery (before 37 weeks of gestation), low birth weight (less than 2.5 kg) and small for gestational age at birth.

Fetal/Neonatal Adverse Reactions

As with other IgG antibodies, infliximab products cross the placenta. Infliximab products have been detected in the serum of infants up to 6 months following birth. Consequently, these infants may be at increased risk of infection, including disseminated infection which can become fatal. At least a six month waiting period following birth is recommended before the administration of live vaccines (e.g., BCG vaccine or other live vaccines, such as the rotavirus vaccine) to these infants [see Warnings and Precautions (5.13)]. Cases of agranulocytosis in infants exposed in utero have also been reported [see Adverse Reactions (6.3)].

Data

Human Data

Two prospective cohort studies were conducted assessing birth outcomes as well as the health status of infants up to the age of one year in women exposed to infliximab compared to non-biologic comparators including methotrexate, azathioprine, 6-mercaptopurine and systemic corticosteroids used for the treatment of similar diseases. The first study was conducted in an IBD pregnancy registry in the United States and assessed pregnancy outcomes in 294 women with inflammatory bowel disease exposed to infliximab during pregnancy compared with 515 women on a non-biologic treatment. Infliximab exposure was not associated with increased rates of major congenital malformations, miscarriage/stillbirth, infants of low birth weight, small for gestational age, or infection in the first year of life. The second study among IBD and non-IBD patients in Sweden, Finland, and Denmark compared 97, 7, and 166 women exposed to infliximab to 2,693, 2,499 and 1,268 women on non-biologic systemic therapy, respectively. In this study, comparing pooled data across the three countries, exposure to infliximab was not associated with increased rates of congenital anomalies or infant death. Infliximab in combination with immunosuppressants (mainly systemic corticosteroids and azathioprine) was associated with increased rates of preterm birth, small for gestational age, low birth weight, and infant hospitalization for infection compared with non-biologic systemic treatment. Although the study did not show any associations with infliximab monotherapy, the analyses could have been underpowered to detect an association. There were additional methodological limitations with these studies that may account for the study findings in both studies: the concomitant use of other medications or treatments was not controlled and disease severity was not assessed; in the U.S. study, patient reported outcomes were collected without clinical validation. These methodological limitations hinder interpretation of the study results.

Animal Data

Because infliximab products do not cross-react with TNFα in species other than humans and chimpanzees, animal reproduction studies have not been conducted with infliximab products. An embryofetal development study was conducted in pregnant mice using cV1q anti-mouse TNFα, an analogous antibody that selectively inhibits the functional activity of mouse TNFα. This antibody administered in mice, during the period of organogenesis on gestation days (GDs) 6 and 12, at IV doses up to 40 mg/kg produced no evidence of maternal toxicity, fetal mortality, or structural abnormalities. Doses of 10 to 15 mg/kg in pharmacodynamic animal models with the anti-TNF analogous antibody produced maximal pharmacologic effectiveness. Analyses of fetal samples on GD 14 indicated placental transfer of the antibody and exposure of the fetuses during organogenesis. In a peri-and post-natal development study in mice, no maternal toxicity or adverse developmental effects in offspring were observed when dams were administered IV doses of 10 or 40 mg/kg of the analogous antibody on GDs 6, 12 and 18 and lactation days 3, 9 and 15.

8.2 Lactation

Risk Summary

Published literature show that infliximab is present at low levels in human milk. Systemic exposure in a breastfed infant is expected to be low because infliximab products are largely degraded in the gastrointestinal tract. A U.S. multi-center study of 168 women treated with infliximab for inflammatory bowel disease (breast milk samples obtained, n=29) showed that infants exposed to infliximab through breast milk had no increase in rates of infections and developed normally. There are no data on the effects of infliximab products on milk production. The developmental and health benefits of breastfeeding should be considered along with the mother's clinical need for INFLECTRA and any potential adverse effects on the breastfed child from INFLECTRA or from the underlying maternal condition.

8.4 Pediatric Use

The safety and effectiveness of INFLECTRA have been established in pediatric patients 6 to 17 years of age for induction and maintenance treatment of CD and UC. [see Dosage and Administration (2.2, 2.4) and Adverse Reactions (6.1)]. However, the safety and effectiveness of INFLECTRA in pediatric patients <6 years of age with CD or UC have not been established. The safety and effectiveness of INFLECTRA in the treatment of pediatric patients with Ps and juvenile rheumatoid arthritis (JRA) have not been established.

Pediatric Crohn's Disease

The safety and effectiveness of INFLECTRA have been established for reducing signs and symptoms and inducing and maintaining clinical remission in pediatric patients 6 years of age and older with moderately to severely active CD who have had an inadequate response to conventional therapy. The use of INFLECTRA for this indication is supported by evidence from a randomized, open-label pediatric CD study of infliximab in 112 pediatric patients aged 6 years and older [see Clinical Studies (14.2)].

Infliximab has been studied only in combination with conventional immunosuppressive therapy in pediatric CD. The longer term (greater than 1 year) safety and effectiveness of infliximab products in pediatric CD patients have not been established in clinical trials.

Postmarketing cases of HSTCL have been reported in pediatric patients treated with TNF blockers including infliximab products. Due to the risk of HSTCL, a careful risk-benefit assessment should be made when INFLECTRA is used in combination with other immunosuppressants in pediatric CD patients [see Boxed Warning, Warnings and Precautions (5.2)].

Pediatric Ulcerative Colitis

The safety and effectiveness of INFLECTRA for reducing signs and symptoms and inducing and maintaining clinical remission in pediatric patients aged 6 years and older with moderately to severely active UC who have had an inadequate response to conventional therapy have been established. The use of INFLECTRA for this indication is supported by evidence from adequate and well-controlled studies of infliximab in adults with additional safety and pharmacokinetic data from an open-label pediatric UC Study in 60 pediatric patients aged 6 years and older [see Dosage and Administration (2.4), Adverse Reactions (6.1), and Clinical Studies (14.4)]. The effectiveness of infliximab in inducing and maintaining mucosal healing in pediatric UC was not established. Although 41 patients had a Mayo endoscopy subscore of 0 or 1 at the Week 8 endoscopy, the induction phase was open-label and lacked a control group. Only 9 patients had an optional endoscopy at Week 54. Approximately half of the patients were on concomitant immunomodulators (AZA, 6-MP, MTX) at study start.

Due to the risk of HSTCL, a careful risk-benefit assessment should be made when INFLECTRA is used in combination with other immunosuppressants in pediatric UC patients [see Boxed Warning and Warnings and Precautions (5.2)].

The longer term (greater than 1 year) safety and effectiveness of infliximab products in pediatric UC patients have not been established in clinical trials.

Juvenile Rheumatoid Arthritis (JRA)

The safety and effectiveness of INFLECTRA in the treatment of pediatric patients with juvenile rheumatoid arthritis (JRA) have not been established.

The safety and efficacy of INFLECTRA in patients with JRA is based on the evaluation of infliximab in a multicenter, randomized, placebo-controlled, double-blind study for 14 weeks, followed by a double-blind, all-active treatment extension, for a maximum of 44 weeks. Patients with active JRA between the ages of 4 and 17 years who had been treated with MTX for at least 3 months were enrolled. Concurrent use of folic acid, oral corticosteroids (≤0.2 mg/kg/day of prednisone or equivalent), NSAIDs, and/or disease modifying antirheumatic drugs (DMARDs) was permitted.

Doses of 3 mg/kg of infliximab or placebo were administered intravenously at Weeks 0, 2 and 6. Patients randomized to placebo crossed-over to receive 6 mg/kg of infliximab at Weeks 14, 16, and 20, and then every 8 weeks through Week 44. Patients who completed the study continued to receive open-label treatment with infliximab for up to 2 years in a companion extension study.

The study failed to establish the efficacy of infliximab in the treatment of JRA. Key observations in the study included a high placebo response rate and a higher rate of immunogenicity than what has been observed in adults. Additionally, a higher rate of clearance of infliximab was observed than had been observed in adults.

Population pharmacokinetic analysis showed that in pediatric patients with JRA with a body weight of up to 35 kg receiving 6 mg/kg infliximab and pediatric patients with JRA with body weight greater than 35 kg up to adult body weight receiving 3 mg/kg infliximab, the steady state area under the concentration curve (AUCss) was similar to that observed in adults receiving 3 mg/kg of infliximab.

A total of 60 patients with JRA were treated with doses of 3 mg/kg and 57 patients were treated with doses of 6 mg/kg. The proportion of patients with infusion reactions who received 3 mg/kg infliximab was 35% (21/60) over 52 weeks compared with 18% (10/57) in patients who received 6 mg/kg over 38 weeks. The most common infusion reactions reported were vomiting, fever, headache, and hypotension. In the 3 mg/kg infliximab group, 4 patients had a serious infusion reaction and 3 patients reported a possible anaphylactic reaction (2 of which were among the serious infusion reactions). In the 6 mg/kg infliximab group, 2 patients had a serious infusion reaction, 1 of whom had a possible anaphylactic reaction. Two of the 6 patients who experienced serious infusion reactions received infliximab by rapid infusion (duration of less than 2 hours). Antibodies to infliximab developed in 38% (20/53) of patients who received 3 mg/kg infliximab compared with 12% (6/49) of patients who received 6 mg/kg.

A total of 68% (41/60) of patients who received 3 mg/kg of infliximab in combination with MTX experienced an infection over 52 weeks compared with 65% (37/57) of patients who received 6 mg/kg of infliximab in combination with MTX over 38 weeks. The most commonly reported infections were upper respiratory tract infection and pharyngitis, and the most commonly reported serious infection was pneumonia. Other notable infections included primary varicella infection in 1 patient and herpes zoster in 1 patient.

8.5 Geriatric Use

Of the total number of infliximab-treated patients in RA and Ps clinical studies, 256 (9.6%) were 65 years old and over, while 17 (0.6%) were 75 years old and over. In these trials, no overall differences in safety or effectiveness were observed between geriatric patients (patients ≥65 years old) and younger adult patients (patients 18 to 65 years old). However, the incidence of serious adverse reactions in geriatric patients was higher in both infliximab and control groups compared to younger adult patients.

Of the total number of infliximab-treated patients in CD, UC, AS, and PsA clinical studies, 76 (3.2%) were 65 years old and over, while 9 (0.4%) were 75 years old and over. In the CD, UC, AS, and PsA studies, there were insufficient numbers of geriatric patients to determine whether they respond differently from younger adults.

The incidence of serious infections in infliximab-treated geriatric patients was greater than in infliximab-treated younger adult patients; therefore close monitoring of geriatric patients for the development of serious infections is recommended [see Warnings and Precautions (5.1), and Adverse Reactions (6.1)].

10 OVERDOSAGE

Single doses up to 20 mg/kg have been administered without any direct toxic effect. In case of overdosage, it is recommended that the patient be monitored for any signs or symptoms of adverse reactions or effects [see Warnings and Precautions (5)] and appropriate symptomatic treatment instituted immediately.

11 DESCRIPTION

Infliximab-dyyb, a tumor necrosis factor (TNF) blocker, is a chimeric IgG1κ monoclonal antibody (composed of human constant and murine variable regions). It has a molecular weight of approximately 149.1 kilodaltons. Infliximab-dyyb is produced by a recombinant murine myeloma cell line, SP2/0.

INFLECTRA (infliximab-dyyb) for injection is supplied as a sterile, preservative-free, white, lyophilized powder for intravenous infusion after reconstitution and dilution. Following reconstitution with 10 mL of Sterile Water for Injection, USP, the final concentration is 10 mg/mL and the resulting pH is approximately 7.2. Each single-dose vial contains 100 mg infliximab-dyyb, dibasic sodium phosphate, dihydrate (6.1 mg), monobasic sodium phosphate, monohydrate (2.2 mg), polysorbate 80 (0.5 mg), and sucrose (500 mg).

12 CLINICAL PHARMACOLOGY

12.1 Mechanism of Action

Infliximab products neutralize the biological activity of TNFα by binding with high affinity to the soluble and transmembrane forms of TNFα and inhibit binding of TNFα with its receptors. Infliximab products do not neutralize TNFβ (lymphotoxin-α), a related cytokine that utilizes the same receptors as TNFα. Biological activities attributed to TNFα include: induction of proinflammatory cytokines such as interleukins (IL) 1 and 6, enhancement of leukocyte migration by increasing endothelial layer permeability and expression of adhesion molecules by endothelial cells and leukocytes, activation of neutrophil and eosinophil functional activity, induction of acute phase reactants and other liver proteins, as well as tissue degrading enzymes produced by synoviocytes and/or chondrocytes. Cells expressing transmembrane TNFα bound by infliximab products can be lysed in vitro or in vivo. Infliximab products inhibit the functional activity of TNFα in a wide variety of in vitro bioassays utilizing human fibroblasts, endothelial cells, neutrophils, B and T lymphocytes and epithelial cells. The relationship of these biological response markers to the mechanism(s) by which infliximab products exert their clinical effects is unknown. Anti-TNFα antibodies reduce disease activity in the cotton-top tamarin colitis model, and decrease synovitis and joint erosions in a murine model of collagen-induced arthritis. Infliximab products prevent disease in transgenic mice that develop polyarthritis as a result of constitutive expression of human TNFα, and when administered after disease onset, allow eroded joints to heal.

12.2 Pharmacodynamics

Elevated concentrations of TNFα have been found in involved tissues and fluids of patients with RA, CD, UC, AS, PsA and Ps. In RA, treatment with infliximab products reduced infiltration of inflammatory cells into inflamed areas of the joint as well as expression of molecules mediating cellular adhesion [E-selectin, intercellular adhesion molecule-1 (ICAM-1) and vascular cell adhesion molecule-1 (VCAM-1)], chemoattraction [IL-8 and monocyte chemotactic protein (MCP-1)] and tissue degradation [matrix metalloproteinase (MMP) 1 and 3]. In CD, treatment with infliximab products reduced infiltration of inflammatory cells and TNFα production in inflamed areas of the intestine, and reduced the proportion of mononuclear cells from the lamina propria able to express TNFα and interferon. After treatment with infliximab products, patients with RA or CD exhibited decreased levels of serum IL-6 and C-reactive protein (CRP) compared to baseline. Peripheral blood lymphocytes from infliximab product-treated patients showed no significant decrease in number or in proliferative responses to in vitro mitogenic stimulation when compared to cells from untreated patients. In PsA, treatment with infliximab products resulted in a reduction in the number of T-cells and blood vessels in the synovium and psoriatic skin lesions as well as a reduction of macrophages in the synovium. In Ps, infliximab products treatment may reduce the epidermal thickness and infiltration of inflammatory cells. The relationship between these pharmacodynamic activities and the mechanism(s) by which infliximab products exert their clinical effects is unknown.

12.3 Pharmacokinetics

In adults, single intravenous (IV) infusions of 3 mg/kg to 20 mg/kg (two times the maximum recommended dose for any indication) of infliximab showed a linear relationship between the dose administered and the maximum serum concentration. The volume of distribution at steady state was independent of dose and indicated that infliximab was distributed primarily within the vascular compartment. Pharmacokinetic results for single doses of 3 mg/kg to 10 mg/kg in RA, 5 mg/kg in CD, and 3 mg/kg to 5 mg/kg in Ps indicate that the median terminal half-life of infliximab is 7.7 to 9.5 days.

Following an initial dose of infliximab, repeated infusions at 2 and 6 weeks resulted in predictable concentration-time profiles following each treatment. No systemic accumulation of infliximab occurred upon continued repeated treatment with 3 mg/kg or 10 mg/kg at 4- or 8-week intervals. Development of antibodies to infliximab increased infliximab clearance. At 8 weeks after a maintenance dose of 3 to 10 mg/kg of infliximab, median infliximab serum concentrations ranged from approximately 0.5 to 6 mcg/mL; however, infliximab concentrations were not detectable (<0.1 mcg/mL) in patients who became positive for antibodies to infliximab. No major differences in clearance or volume of distribution were observed in patient subgroups defined by age, weight, or gender. It is not known if there are differences in clearance or volume of distribution in patients with marked impairment of hepatic or renal function.

Infliximab pharmacokinetic characteristics (including peak and trough concentrations and terminal half-life) were similar in pediatric (aged 6 to 17 years) and adult patients with CD or UC following the administration of 5 mg/kg of infliximab.

13 NONCLINICAL TOXICOLOGY

13.1 Carcinogenesis, Mutagenesis, Impairment of Fertility

A 6-month study in CD-1 mice was conducted to assess the tumorigenic potential of cV1q anti-mouse TNFα, an analogous antibody. No evidence of tumorigenicity was observed in mice that received intravenous doses of 10 mg/kg or 40 mg/kg cV1q given weekly. The relevance of this study for human risk is unknown. No impairment of fertility or reproductive performance indices were observed in male or female mice that received cV1q, an analogous mouse antibody, at intravenous doses up to 40 mg/kg given weekly.

14 CLINICAL STUDIES

14.1 Adult Crohn's Disease

Active Crohn's Disease in Adults

The safety and efficacy of single and multiple doses of infliximab were assessed in 2 randomized, double-blind, placebo-controlled clinical studies in 653 adult patients with moderate to severely active CD [Crohn's Disease Activity Index (CDAI) ≥220 and ≤400] with an inadequate response to prior conventional therapies. Concomitant stable doses of aminosalicylates, corticosteroids and/or immunomodulatory agents were permitted and 92% of patients continued to receive at least one of these medications.

In the single-dose trial of 108 adult patients, 16% (4/25) of placebo patients achieved a clinical response (decrease in CDAI ≥70 points) at Week 4 vs. 81% (22/27) of patients receiving 5 mg/kg infliximab (P<0.001, two-sided, Fisher's Exact test). Additionally, 4% (1/25) of placebo patients and 48% (13/27) of patients receiving 5 mg/kg of infliximab achieved clinical remission (CDAI<150) at Week 4.

In a multidose trial (ACCENT I [Study Crohn's I]), 545 adult patients received 5 mg/kg at Week 0 and were then randomized to one of three treatment groups; the placebo maintenance group received placebo at Weeks 2 and 6, and then every 8 weeks; the 5 mg/kg maintenance group received 5 mg/kg at Weeks 2 and 6, and then every 8 weeks; and the 10 mg/kg maintenance group received 5 mg/kg at Weeks 2 and 6, and then 10 mg/kg every 8 weeks. Patients in response at Week 2 were randomized and analyzed separately from those not in responses at Week 2. Corticosteroid taper was permitted after Week 6.

At Week 2, 57% (311/545) of patients were in clinical response. At Week 30, a significantly greater proportion of these patients in the 5 mg/kg and 10 mg/kg maintenance groups achieved clinical remission compared to patients in the placebo maintenance group (Table 3).

Additionally, a significantly greater proportion of patients in the 5 mg/kg and 10 mg/kg infliximab maintenance groups were in clinical remission and were able to discontinue corticosteroid use compared to patients in the placebo maintenance group at Week 54 (Table 3).

Table 3 Clinical Remission and Steroid Withdrawal in Adult Patients with CD (Study Crohn's I)
 | Single 5-mg/kg Dose [Infliximab at Week 0] | Three-Dose Induction [Infliximab 5 mg/kg administered at Weeks 0, 2 and 6]
 | Placebo Maintenance | Infliximab Maintenance q 8wks
 |  | 5 mg/kg | 10 mg/kg
Week 30
Clinical remission | 25/102 25% | 41/104 39% | 48/105 46%
P-value [P-values represent pairwise comparisons to placebo] |  | 0.022 | 0.001
Week 54
Patients in remission able to discontinue corticosteroid use [Of those receiving corticosteroids at baseline] | 6/54 11% | 14/56 25% | 18/53 34%
P-value |  | 0.059 | 0.005

Patients in the infliximab maintenance groups (5 mg/kg and 10 mg/kg) had a longer time to loss of response than patients in the placebo maintenance group (Figure 1). At Weeks 30 and 54, significant improvement from baseline was seen among the 5 mg/kg and 10 mg/kg groups treated with infliximab compared to the placebo group in the disease-specific inflammatory bowel disease questionnaire (IBDQ), particularly the bowel and systemic components, and in the physical component summary score of the general health-related quality of life questionnaire SF-36.

Figure 1 Kaplan-Meier Estimate of the Proportion of Adults with CD Who Had Not Lost Response Through Week 54 (Study Crohn's I)

In a subset of 78 patients who had mucosal ulceration at baseline and who participated in an endoscopic substudy, 13 of 43 patients in infliximab maintenance group had endoscopic evidence of mucosal healing compared to 1 of 28 patients in the placebo group at Week 10. Of the patients treated with infliximab showing mucosal healing at Week 10, 9 of 12 patients also showed mucosal healing at Week 54.

Patients who achieved a response and subsequently lost response were eligible to receive infliximab on an episodic basis at a dose that was 5 mg/kg higher than the dose to which they were randomized. The majority of such patients responded to the higher dose. Among patients who were not in response at Week 2, 59% (92/157) of maintenance patients on infliximab responded by Week 14 compared to 51% (39/77) of placebo maintenance patients. Among patients who did not respond by Week 14, additional therapy did not result in significantly more responses [see Dosage and Administration (2)].

Fistulizing Crohn's Disease in Adults

The safety and efficacy of infliximab were assessed in 2 randomized, double-blind, placebo-controlled studies in adult patients with fistulizing CD with fistula(s) that were of at least 3 months duration. Concurrent use of stable doses of corticosteroids, 5-aminosalicylates, antibiotics, MTX, 6-MP and/or AZA was permitted.

In the first trial, 94 adult patients received 3 doses of either placebo or infliximab at Weeks 0, 2 and 6. Fistula response (≥50% reduction in number of enterocutaneous fistulas draining upon gentle compression on at least 2 consecutive visits without an increase in medication or surgery for CD) was seen in 68% (21/31) of patients in the 5 mg/kg infliximab group (P=0.002) and 56% (18/32) of patients in the 10 mg/kg infliximab group (P=0.021) vs. 26% (8/31) of patients in the placebo arm. The median time to onset of response and median duration of response in patients treated with infliximab was 2 and 12 weeks, respectively. Closure of all fistulas was achieved in 52% patients treated with infliximab compared with 13% of placebo-treated patients (P<0.001).

In the second trial (ACCENT II [Study Crohn's II]), adult patients who were enrolled had to have at least 1 draining enterocutaneous (perianal, abdominal) fistula. All patients received 5 mg/kg of infliximab at Weeks 0, 2 and 6. Patients were randomized to placebo or 5 mg/kg maintenance with infliximab at Week 14. Patients received maintenance doses at Week 14 and then every 8 weeks through Week 46. Patients who were in fistula response (fistula response was defined the same as in the first trial) at both Weeks 10 and 14 were randomized separately from those not in response. The primary endpoint was time from randomization to loss of response among those patients who were in fistula response.

Among the randomized patients (273 of the 296 initially enrolled), 87% had perianal fistulas and 14% had abdominal fistulas. Eight percent also had rectovaginal fistulas. Greater than 90% of the patients had received previous immunosuppressive and antibiotic therapy.

At Week 14, 65% (177/273) of patients were in fistula response. Patients randomized to maintenance with infliximab had a longer time to loss of fistula response compared to the placebo maintenance group (Figure 2). At Week 54, 38% (33/87) of patients treated with infliximab had no draining fistulas compared with 22% (20/90) of placebo-treated patients (P=0.02). Compared to placebo maintenance, patients on maintenance treatment with infliximab had a trend toward fewer hospitalizations.

Figure 2 Life Table Estimates of the Proportion of Adult CD Patients Who Had Not Lost Fistula Response Through Week 54 (Study Crohn's II)

Patients who achieved a fistula response and subsequently lost response were eligible to receive maintenance therapy with infliximab at a dose that was 5 mg/kg higher than the dose to which they were randomized. Of the placebo maintenance patients, 66% (25/38) responded to 5 mg/kg infliximab, and 57% (12/21) of maintenance patients on infliximab responded to 10 mg/kg.

Patients who had not achieved a response by Week 14 were unlikely to respond to additional doses of infliximab.

Similar proportions of patients in either group developed new fistulas (17% overall) and similar numbers developed abscesses (15% overall).

14.2 Pediatric Crohn's Disease

The safety and efficacy of infliximab were assessed in a randomized, open-label study (Study Peds Crohn's) in 112 pediatric patients aged 6 to 17 years old with moderately to severely active CD and an inadequate response to conventional therapies. The median age was 13 years and the median Pediatric Crohn's Disease Activity Index (PCDAI) was 40 (on a scale of 0 to 100). All patients were required to be on a stable dose of 6-MP, AZA, or MTX; 35% were also receiving corticosteroids at baseline.

All patients received induction dosing of 5 mg/kg of infliximab at Weeks 0, 2, and 6. At Week 10, 103 patients were randomized to a maintenance regimen of 5 mg/kg of infliximab given either every 8 weeks or every 12 weeks.

At Week 10, 88% of patients were in clinical response (defined as a decrease from baseline in the PCDAI score of ≥15 points and total PCDAI score of ≤30 points), and 59% were in clinical remission (defined as PCDAI score of ≤10 points).

The proportion of pediatric patients achieving clinical response at Week 10 compared favorably with the proportion of adults achieving a clinical response in Study Crohn's I. The study definition of clinical response in Study Peds Crohn's was based on the PCDAI score, whereas the CDAI score was used in the adult Study Crohn's I.

At both Week 30 and Week 54, the proportion of patients in clinical response was greater in the every 8-week treatment group than in the every 12-week treatment group (73% vs. 47% at Week 30, and 64% vs. 33% at Week 54). At both Week 30 and Week 54, the proportion of patients in clinical remission was also greater in the every 8-week treatment group than in the every 12-week treatment group (60% vs. 35% at Week 30, and 56% vs. 24% at Week 54), (Table 4).

For patients in Study Peds Crohn's receiving corticosteroids at baseline, the proportion of patients able to discontinue corticosteroids while in remission at Week 30 was 46% for the every 8-week maintenance group and 33% for the every 12-week maintenance group. At Week 54, the proportion of patients able to discontinue corticosteroids while in remission was 46% for the every 8-week maintenance group and 17% for the every 12-week maintenance group.

Table 4 Response and Remission in Study Peds Crohn's
 | 5 mg/kg Infliximab
 | Every 8 Week Treatment Group | Every 12 Week Treatment Group
Patients randomized | 52 | 51
Clinical Response [Defined as a decrease from baseline in the PCDAI score of ≥15 points and total score of ≤30 points.]
Week 30 | 73% [P-value <0.01] | 47%
Week 54 | 64% | 33%
Clinical Remission [Defined as a PCDAI score of ≤10 points.]
Week 30 | 60% [P-value <0.05] | 35%
Week 54 | 56% | 24%

14.3 Adult Ulcerative Colitis

The safety and efficacy of infliximab were assessed in 2 randomized, double-blind, placebo-controlled clinical studies in 728 adult patients with moderately to severely active UC (Mayo score 6 to 12 [of possible range 0 to 12], Endoscopy subscore ≥2) with an inadequate response to conventional oral therapies (Studies UC I and UC II). Concomitant treatment with stable doses of aminosalicylates, corticosteroids and/or immunomodulatory agents was permitted. Corticosteroid taper was permitted after Week 8. Patients were randomized at Week 0 to receive either placebo, 5 mg/kg infliximab or 10 mg/kg infliximab at Weeks 0, 2, 6, and every 8 weeks thereafter through Week 46 in Study UC I, and at Weeks 0, 2, 6, and every 8 weeks thereafter through Week 22 in Study UC II. In Study UC II, patients were allowed to continue blinded therapy to Week 46 at the investigator's discretion.

Adult patients in Study UC I had failed to respond or were intolerant to oral corticosteroids, 6-MP, or AZA. Adult patients in Study UC II had failed to respond or were intolerant to the above treatments and/or aminosalicylates. Similar proportions of patients in Studies UC I and UC II were receiving corticosteroids (61% and 51%, respectively), 6-MP/AZA (49% and 43%) and aminosalicylates (70% and 75%) at baseline. More patients in Study UC II than UC I were taking solely aminosalicylates for UC (26% vs. 11%, respectively). Clinical response was defined as a decrease from baseline in the Mayo score by ≥30% and ≥3 points, accompanied by a decrease in the rectal bleeding subscore of ≥1 or a rectal bleeding subscore of 0 or 1.

Clinical Response, Clinical Remission, and Mucosal Healing

In both Study UC I and Study UC II, greater percentages of patients in both infliximab groups achieved clinical response, clinical remission and mucosal healing than in the placebo group. Each of these effects was maintained through the end of each trial (Week 54 in Study UC I, and Week 30 in Study UC II). In addition, a greater proportion of patients in infliximab groups demonstrated sustained response and sustained remission than in the placebo groups (Table 5).

Of patients on corticosteroids at baseline, greater proportions of adult patients in groups treated with infliximab were in clinical remission and able to discontinue corticosteroids at Week 30 compared with the patients in the placebo treatment groups (22% in infliximab treatment groups vs. 10% in placebo group in Study UC I; 23% in infliximab treatment groups vs. 3% in placebo group in Study UC II). In Study UC I, this effect was maintained through Week 54 (21% in infliximab treatment groups vs. 9% in placebo group). The infliximab-associated response was generally similar in the 5 mg/kg and 10 mg/kg dose groups.

Table 5 Response, Remission and Mucosal Healing in Adult UC Studies (Studies UC I and UC II)
 | Study UC I |  |  | Study UC II
 | Placebo | 5 mg/kg Infliximab | 10 mg/kg Infliximab | Placebo | 5 mg/kg Infliximab | 10 mg/kg Infliximab
Patients randomized | 121 | 121 | 122 | 123 | 121 | 120
Clinical Response [Defined as a decrease from baseline in the Mayo score by ≥30% and ≥3 points, accompanied by a decrease in the rectal bleeding subscore of ≥1 or a rectal bleeding subscore of 0 or 1. (The Mayo score consists of the sum of four subscores: stool frequency, rectal bleeding, physician's global assessment and endoscopy findings).] , [Patients who had a prohibited change in medication, had an ostomy or colectomy, or discontinued study infusions due to lack of efficacy are considered to not be in clinical response, clinical remission or mucosal healing from the time of the event onward.]
Week 8 | 37% | 69% [P<0.001,] | 62% | 29% | 65% | 69%
Week 30 | 30% | 52% | 51% [P<0.01] | 26% | 47% | 60%
Week 54 | 20% | 45% | 44% | NA | NA | NA
Sustained Response
(Clinical response at both Week 8 and 30) | 23% | 49% | 46% | 15% | 41% | 53%
(Clinical response at Weeks 8, 30 and 54) | 14% | 39% | 37% | NA | NA | NA
Clinical Remission [Defined as a Mayo score ≤2 points, no individual subscore >1.] ,
Week 8 | 15% | 39% | 32% | 6% | 34% | 28%
Week 30 | 16% | 34% | 37% | 11% | 26% | 36%
Week 54 | 17% | 35% | 34% | NA | NA | NA
Sustained Remission
(Clinical remission at both Week 8 and 30) | 8% | 23% | 26% | 2% | 15% | 23%
(Clinical remission at Weeks 8, 30 and 54) | 7% | 20% | 20% | NA | NA | NA
Mucosal Healing [Defined as a 0 or 1 on the endoscopy subscore of the Mayo score.] ,
Week 8 | 34% | 62% | 59% | 31% | 60% | 62%
Week 30 | 25% | 50% | 49% | 30% | 46% | 57%
Week 54 | 18% | 45% | 47% | NA | NA | NA

The improvement with infliximab was consistent across all Mayo subscores through Week 54 (Study UC I shown in Table 6; Study UC II through Week 30 was similar).

Table 6 Proportion of Adult UC Patients in Study UC I with Mayo Subscores Indicating Inactive or Mild Disease Through Week 54
 | Study UC I
 |  | Infliximab
 | Placebo (n=121) | 5 mg/kg (n=121) | 10 mg/kg (n=122)
Stool frequency
Baseline | 17% | 17% | 10%
Week 8 | 35% | 60% | 58%
Week 30 | 35% | 51% | 53%
Week 54 | 31% | 52% | 51%
Rectal bleeding
Baseline | 54% | 40% | 48%
Week 8 | 74% | 86% | 80%
Week 30 | 65% | 74% | 71%
Week 54 | 62% | 69% | 67%
Physician's Global Assessment
Baseline | 4% | 6% | 3%
Week 8 | 44% | 74% | 64%
Week 30 | 36% | 57% | 55%
Week 54 | 26% | 53% | 53%
Endoscopy findings
Baseline | 0% | 0% | 0%
Week 8 | 34% | 62% | 59%
Week 30 | 26% | 51% | 52%
Week 54 | 21% | 50% | 51%

14.4 Pediatric Ulcerative Colitis

The safety and effectiveness of infliximab products for reducing signs and symptoms and inducing and maintaining clinical remission in pediatric patients aged 6 years and older with moderately to severely active UC who have had an inadequate response to conventional therapy are supported by evidence from adequate and well-controlled studies of infliximab in adults. Additional safety and pharmacokinetic data were collected in an open-label pediatric UC trial in 60 pediatric patients aged 6 through 17 years (median age 14.5 years) with moderately to severely active UC (Mayo score of 6 to 12; Endoscopic subscore ≥2) and an inadequate response to conventional therapies. At baseline, the median Mayo score was 8, 53% of patients were receiving immunomodulator therapy (6-MP/AZA/MTX), and 62% of patients were receiving corticosteroids (median dose 0.5 mg/kg/day in prednisone equivalents). Discontinuation of immunomodulators and corticosteroid taper were permitted after Week 0.

All patients received induction dosing of 5 mg/kg infliximab at Weeks 0, 2, and 6. Patients who did not respond to infliximab at Week 8 received no further infliximab and returned for safety follow-up. At Week 8, 45 patients were randomized to a maintenance regimen of 5 mg/kg infliximab given either every 8 weeks through Week 46 or every 12 weeks through Week 42. Patients were allowed to change to a higher dose and/or more frequent administration schedule if they experienced loss of response.

Clinical response at Week 8 was defined as a decrease from baseline in the Mayo score by ≥30% and ≥3 points, including a decrease in the rectal bleeding subscore by ≥1 points or achievement of a rectal bleeding subscore of 0 or 1.

Clinical remission at Week 8 was measured by the Mayo score, defined as a Mayo score of ≤2 points with no individual subscore >1. Clinical remission was also assessed at Week 8 and Week 54 using the Pediatric Ulcerative Colitis Activity Index (PUCAI)^1 score and was defined by a PUCAI score of <10 points.

Endoscopies were performed at baseline and at Week 8. A Mayo endoscopy subscore of 0 indicated normal or inactive disease and a subscore of 1 indicated mild disease (erythema, decreased vascular pattern, or mild friability).

Of the 60 patients treated, 44 were in clinical response at Week 8. Of 32 patients taking concomitant immunomodulators at baseline, 23 achieved clinical response at Week 8, compared to 21 of 28 of those not taking concomitant immunomodulators at baseline. At Week 8, 24 of 60 patients were in clinical remission as measured by the Mayo score and 17 of 51 patients were in remission as measured by the PUCAI score.

At Week 54, 8 of 21 patients in the every 8-week maintenance group and 4 of 22 patients in the every 12-week maintenance group achieved remission as measured by the PUCAI score.

During maintenance phase, 23 of 45 randomized patients (9 in the every 8-week group and 14 in the every 12-week group) required an increase in their dose and/or increase in frequency of infliximab administration due to loss of response. Nine of the 23 patients who required a change in dose had achieved remission at Week 54. Seven of those patients received the 10 mg/kg every 8-week dosing.

14.5 Rheumatoid Arthritis

The safety and efficacy of infliximab in adult patients with RA were assessed in 2 multicenter, randomized, double-blind, pivotal trials: ATTRACT (Study RA I) and ASPIRE (Study RA II). Concurrent use of stable doses of folic acid, oral corticosteroids (≤10 mg/day) and/or non-steroidal anti-inflammatory drugs (NSAIDs) was permitted.

Study RA I was a placebo-controlled study of 428 patients with active RA despite treatment with MTX. Patients enrolled had a median age of 54 years, median disease duration of 8.4 years, median swollen and tender joint count of 20 and 31 respectively, and were on a median dose of 15 mg/wk of MTX. Patients received either placebo+MTX or one of 4 doses/schedules of the infliximab+MTX: 3 mg/kg or 10 mg/kg infliximab by IV infusion at Weeks 0, 2 and 6 followed by additional infusions every 4 or 8 weeks in combination with MTX.

Study RA II was a placebo-controlled study of 3 active treatment arms in 1004 MTX naïve patients of 3 or fewer years' duration active RA. Patients enrolled had a median age of 51 years with a median disease duration of 0.6 years, median swollen and tender joint count of 19 and 31, respectively, and >80% of patients had baseline joint erosions. At randomization, all patients received MTX (optimized to 20 mg/wk by Week 8) and either placebo, 3 mg/kg or 6 mg/kg of infliximab at Weeks 0, 2, and 6 and every 8 weeks thereafter.

Data on use of infliximab products without concurrent MTX are limited [see Adverse Reactions (6.1)].

Clinical Response

In Study RA I, all doses/schedules of infliximab+MTX resulted in improvement in signs and symptoms as measured by the American College of Rheumatology response criteria (ACR 20) with a higher percentage of patients achieving an ACR 20, 50 and 70 compared to placebo+MTX (Table 7). This improvement was observed at Week 2 and maintained through Week 102. Greater effects on each component of the ACR 20 were observed in all patients treated with infliximab+MTX compared to placebo+MTX (Table 8). More patients treated with infliximab reached a major clinical response than placebo-treated patients (Table 7).

In Study RA II, after 54 weeks of treatment, both doses of infliximab+MTX resulted in statistically significantly greater response in signs and symptoms compared to MTX alone as measured by the proportion of patients achieving ACR 20, 50 and 70 responses (Table 7). More patients treated with infliximab reached a major clinical response than placebo-treated patients (Table 7).

Table 7 ACR Response (percent of patients) in Adult RA Patients (Studies RA I and RA II)
 | Study RA I |  |  |  |  |  | Study RA II
 |  | Infliximab+MTX |  |  |  |  |  | Infliximab+MTX
 |  | 3 mg/kg |  | 10 mg/kg |  |  |  | 3 mg/kg | 6 mg/kg
Response | Placebo +MTX (n=88) | q8 wks (n=86) | q4 wks (n=86) | q8 wks (n=87) | q4 wks (n=81) |  | Placebo +MTX (n=274) | q8 wks (n=351) | q8 wks (n=355)
ACR 20
Week 30 | 20% | 50% [P≤0.001] | 50% | 52% | 58% |  | N/A | N/A | N/A
Week 54 | 17% | 42% | 48% | 59% | 59% |  | 54% | 62% [P<0.05] | 66%
ACR 50
Week 30 | 5% | 27% | 29% | 31% | 26% |  | N/A | N/A | N/A
Week 54 | 9% | 21% | 34% | 40% | 38% |  | 32% | 46% | 50%
ACR 70
Week 30 | 0% | 8% [P<0.01] | 11% | 18% | 11% |  | N/A | N/A | N/A
Week 54 | 2% | 11% | 18% | 26% | 19% |  | 21% | 33% | 37%
Major clinical response [A major clinical response was defined as a 70% ACR response for 6 consecutive months (consecutive visits spanning at least 26 weeks) through Week 102 for Study RA I and Week 54 for Study RA II.] | 0% | 7% | 8% | 15% | 6% |  | 8% | 12% | 17%

Table 8 Components of ACR 20 at Baseline and 54 Weeks (Study RA I)
 | Placebo+MTX (n=88) |  | Infliximab+MTX [All doses/schedules of infliximab+MTX] (n=340)
Parameter (medians) | Baseline | Week 54 | Baseline | Week 54
No. of Tender Joints | 24 | 16 | 32 | 8
No. of Swollen Joints | 19 | 13 | 20 | 7
Pain [Visual Analog Scale (0=best, 10=worst)] | 6.7 | 6.1 | 6.8 | 3.3
Physician's Global Assessment | 6.5 | 5.2 | 6.2 | 2.1
Patient's Global Assessment | 6.2 | 6.2 | 6.3 | 3.2
Disability Index (HAQ-DI) [Health Assessment Questionnaire, measurement of 8 categories: dressing and grooming, arising, eating, walking, hygiene, reach, grip, and activities (0=best, 3=worst)] | 1.8 | 1.5 | 1.8 | 1.3
CRP (mg/dL) | 3.0 | 2.3 | 2.4 | 0.6

Radiographic Response

Structural damage in both hands and feet was assessed radiographically at Week 54 by the change from baseline in the van der Heijde-modified Sharp (vdH-S) score, a composite score of structural damage that measures the number and size of joint erosions and the degree of joint space narrowing in hands/wrists and feet.

In Study RA I, approximately 80% of patients had paired X-ray data at 54 weeks and approximately 70% at 102 weeks. The inhibition of progression of structural damage was observed at 54 weeks (Table 9) and maintained through 102 weeks.

In Study RA II, >90% of patients had at least 2 evaluable X-rays. Inhibition of progression of structural damage was observed at Weeks 30 and 54 (Table 9) in infliximab+MTX groups compared to MTX alone. Patients treated with infliximab+MTX demonstrated less progression of structural damage compared to MTX alone, whether baseline acute-phase reactants (ESR and CRP) were normal or elevated: patients with elevated baseline acute-phase reactants treated with MTX alone demonstrated a mean progression in vdH-S score of 4.2 units compared to patients treated with infliximab+MTX who demonstrated 0.5 units of progression; patients with normal baseline acute phase reactants treated with MTX alone demonstrated a mean progression in vdH-S score of 1.8 units compared to infliximab+MTX who demonstrated 0.2 units of progression. Of patients receiving infliximab+MTX, 59% had no progression (vdH-S score ≤0 unit) of structural damage compared to 45% of patients receiving MTX alone. In a subset of patients who began the study without erosions, infliximab+MTX maintained an erosion-free state at 1 year in a greater proportion of patients than MTX alone, 79% (77/98) vs. 58% (23/40), respectively (P<0.01). Fewer patients in infliximab+MTX groups (47%) developed erosions in uninvolved joints compared to MTX alone (59%).

Table 9 Radiographic Change from Baseline to Week 54 in Adult RA Patients (Studies RA I and RA II)
 | Study RA I |  |  |  | Study RA II
 |  | Infliximab+MTX |  |  |  | Infliximab+MTX
 |  | 3 mg/kg | 10 mg/kg |  |  | 3 mg/kg | 6 mg/kg
 | Placebo + MTX (n=64) | q8 wks (n=71) | q8 wks (n=77) |  | Placebo + MTX (n=282) | q8 wks (n=359) | q8 wks (n=363)
Total Score
Baseline
Mean | 79 | 78 | 65 |  | 11.3 | 11.6 | 11.2
Median | 55 | 57 | 56 |  | 5.1 | 5.2 | 5.3
Change from baseline
Mean | 6.9 | 1.3 [P<0.001 for each outcome against placebo.] | 0.2 |  | 3.7 | 0.4 | 0.5
Median | 4.0 | 0.5 | 0.5 |  | 0.4 | 0.0 | 0.0
Erosion Score
Baseline
Mean | 44 | 44 | 33 |  | 8.3 | 8.8 | 8.3
Median | 25 | 29 | 22 |  | 3.0 | 3.8 | 3.8
Change from baseline
Mean | 4.1 | 0.2 | 0.2 |  | 3.0 | 0.3 | 0.1
Median | 2.0 | 0.0 | 0.5 |  | 0.3 | 0.0 | 0.0
JSN Score
Baseline
Mean | 36 | 34 | 31 |  | 3.0 | 2.9 | 2.9
Median | 26 | 29 | 24 |  | 1.0 | 1.0 | 1.0
Change from baseline
Mean | 2.9 | 1.1 | 0.0 |  | 0.6 | 0.1 | 0.2
Median | 1.5 | 0.0 | 0.0 |  | 0.0 | 0.0 | 0.0

Physical Function Response

Physical function and disability were assessed using the Health Assessment Questionnaire (HAQ-DI) and the general health-related quality of life questionnaire SF-36.

In Study RA I, all doses/schedules of infliximab+MTX showed significantly greater improvement from baseline in HAQ-DI and SF-36 physical component summary score averaged over time through Week 54 compared to placebo+MTX, and no worsening in the SF-36 mental component summary score. The median (interquartile range) improvement from baseline to Week 54 in HAQ-DI was 0.1 (-0.1, 0.5) for the placebo+MTX group and 0.4 (0.1, 0.9) for infliximab+MTX (p<0.001). Both HAQ-DI and SF-36 effects were maintained through Week 102. Approximately 80% of patients in all doses/schedules of infliximab+MTX remained in the trial through 102 weeks.

In Study RA II, both treatment groups of infliximab showed greater improvement in HAQ-DI from baseline averaged over time through Week 54 compared to MTX alone; 0.7 for infliximab+MTX vs. 0.6 for MTX alone (P≤0.001). No worsening in the SF-36 mental component summary score was observed.

14.6 Ankylosing Spondylitis

The safety and efficacy of infliximab were assessed in a randomized, multicenter, double-blind, placebo-controlled study in 279 adult patients with active AS. Patients were between 18 and 74 years of age, and had AS as defined by the modified New York criteria for Ankylosing Spondylitis. Patients were to have had active disease as evidenced by both a Bath Ankylosing Spondylitis Disease Activity Index (BASDAI) score >4 (possible range 0–10) and spinal pain >4 (on a Visual Analog Scale [VAS] of 0–10). Patients with complete ankylosis of the spine were excluded from study participation, and the use of Disease Modifying Anti-Rheumatic Drugs (DMARDs) and systemic corticosteroids were prohibited. Doses of 5 mg/kg of infliximab or placebo were administered intravenously at Weeks 0, 2, 6, 12 and 18.

At 24 weeks, improvement in the signs and symptoms of AS, as measured by the proportion of patients achieving a 20% improvement in ASAS response criteria (ASAS 20), was seen in 60% of patients in the infliximab-treated group vs. 18% of patients in the placebo group (p<0.001). Improvement was observed at Week 2 and maintained through Week 24 (Figure 3 and Table 10).

Figure 3 Proportion of Adult AS Patients Who Achieved ASAS 20 Response

At 24 weeks, the proportions of patients achieving a 50% and a 70% improvement in the signs and symptoms of AS, as measured by ASAS response criteria (ASAS 50 and ASAS 70, respectively), were 44% and 28%, respectively, for patients receiving infliximab, compared to 9% and 4%, respectively, for patients receiving placebo (P<0.001, infliximab vs. placebo). A low level of disease activity (defined as a value <20 [on a scale of 0 – 100 mm] in each of the 4 ASAS response parameters) was achieved in 22% of patients treated with infliximab vs. 1% in placebo-treated patients (P<0.001).

Table 10 Components of AS Disease Activity
 | Placebo (n=78) |  | Infliximab 5 mg/kg (n=201)
 | Baseline | 24 Weeks | Baseline | 24 Weeks | P-value
ASAS 20 response
Criteria (Mean)
Patient Global Assessment [Measured on a VAS with 0="none" and 10="severe"] | 6.6 | 6.0 | 6.8 | 3.8 | <0.001
Spinal pain | 7.3 | 6.5 | 7.6 | 4.0 | <0.001
BASFI [Bath Ankylosing Spondylitis Functional Index (BASFI), average of 10 questions] | 5.8 | 5.6 | 5.7 | 3.6 | <0.001
Inflammation [Inflammation, average of last 2 questions on the 6-question BASDAI] | 6.9 | 5.8 | 6.9 | 3.4 | <0.001
Acute Phase Reactants
Median CRP [CRP normal range 0–1.0 mg/dL] (mg/dL) | 1.7 | 1.5 | 1.5 | 0.4 | <0.001
Spinal Mobility (cm, Mean)
Modified Schober's test [Spinal mobility normal values: modified Schober's test: >4 cm; chest expansion:>6 cm; tragus to wall: <15 cm; lateral spinal flexion: >10 cm] | 4.0 | 5.0 | 4.3 | 4.4 | 0.75
Chest expansion | 3.6 | 3.7 | 3.3 | 3.9 | 0.04
Tragus to wall | 17.3 | 17.4 | 16.9 | 15.7 | 0.02
Lateral spinal flexion | 10.6 | 11.0 | 11.4 | 12.9 | 0.03

The median improvement from baseline in the general health-related quality-of-life questionnaire SF-36 physical component summary score at Week 24 was 10.2 for the infliximab group vs. 0.8 for the placebo group (P<0.001). There was no change in the SF-36 mental component summary score in either the infliximab group or the placebo group.

Results of this study were similar to those seen in a multicenter double-blind, placebo-controlled study of 70 patients with AS.

14.7 Psoriatic Arthritis

Safety and efficacy of infliximab were assessed in a multicenter, double-blind, placebo-controlled study in 200 adult patients with active PsA despite DMARD or NSAID therapy (≥5 swollen joints and ≥5 tender joints) with 1 or more of the following subtypes: arthritis involving DIP joints (n=49), arthritis mutilans (n=3), asymmetric peripheral arthritis (n=40), polyarticular arthritis (n=100), and spondylitis with peripheral arthritis (n=8). Patients also had Ps with a qualifying target lesion ≥2 cm in diameter. Forty-six percent of patients continued on stable doses of methotrexate (≤25 mg/week). During the 24-week double-blind phase, patients received either 5 mg/kg infliximab or placebo at Weeks 0, 2, 6, 14, and 22 (100 patients in each group). At Week 16, placebo patients with <10% improvement from baseline in both swollen and tender joint counts were switched to infliximab induction (early escape). At Week 24, all placebo-treated patients crossed over to infliximab induction. Dosing continued for all patients through Week 46.

Clinical Response

Treatment with infliximab resulted in improvement in signs and symptoms, as assessed by the ACR criteria, with 58% of patients treated with infliximab achieving ACR 20 at Week 14, compared with 11% of placebo-treated patients (P<0.001). The response was similar regardless of concomitant use of methotrexate. Improvement was observed as early as Week 2. At 6 months, the ACR 20/50/70 responses were achieved by 54%, 41%, and 27%, respectively, of patients receiving infliximab compared to 16%, 4%, and 2%, respectively, of patients receiving placebo. Similar responses were seen in patients with each of the subtypes of PsA, although few patients were enrolled with the arthritis mutilans and spondylitis with peripheral arthritis subtypes.

Compared to placebo, treatment with infliximab resulted in improvements in the components of the ACR response criteria, as well as in dactylitis and enthesopathy (Table 11). The clinical response was maintained through Week 54. Similar ACR responses were observed in an earlier randomized, placebo-controlled study of 104 PsA patients, and the responses were maintained through 98 weeks in an open-label extension phase.

Table 11 Components of ACR 20 and Percentage of Adult PsA Patients with 1 or More Joints with Dactylitis and Percentage of Adult PsA Patients with Enthesopathy at Baseline and Week 24
Patients Randomized | Placebo (n=100) |  | Infliximab 5 mg/kg [P<0.001 for percent change from baseline in all components of ACR 20 at Week 24, P<0.05 for % of patients with dactylitis, and P=0.004 for % of patients with enthesopathy at Week 24] (n=100)
 | Baseline | Week 24 | Baseline | Week 24
Parameter (medians)
No. of Tender Joints [Scale 0–68] | 24 | 20 | 20 | 6
No. of Swollen Joints [Scale 0–66] | 12 | 9 | 12 | 3
Pain [Visual Analog Scale (0=best, 10=worst)] | 6.4 | 5.6 | 5.9 | 2.6
Physician's Global Assessment | 6.0 | 4.5 | 5.6 | 1.5
Patient's Global Assessment | 6.1 | 5.0 | 5.9 | 2.5
Disability Index (HAQ-DI) [Health Assessment Questionnaire, measurement of 8 categories: dressing and grooming, arising, eating, walking, hygiene, reach, grip, and activities (0=best, 3=worst)] | 1.1 | 1.1 | 1.1 | 0.5
CRP (mg/dL) [Normal range 0–0.6 mg/dL] | 1.2 | 0.9 | 1.0 | 0.4
% Patients with 1 or more digits with dactylitis | 41 | 33 | 40 | 15
% Patients with enthesopathy | 35 | 36 | 42 | 22

Improvement in Psoriasis Area and Severity Index (PASI) in PsA patients with baseline body surface area (BSA) ≥3% (n=87 placebo, n=83 infliximab) was achieved at Week 14, regardless of concomitant methotrexate use, with 64% of patients treated with infliximab achieving at least 75% improvement from baseline vs. 2% of placebo-treated patients; improvement was observed in some patients as early as Week 2. At 6 months, the PASI 75 and PASI 90 responses were achieved by 60% and 39%, respectively, of patients receiving infliximab compared to 1% and 0%, respectively, of patients receiving placebo. The PASI response was generally maintained through Week 54. [See Clinical Studies (14.8)].

Radiographic Response

Structural damage in both hands and feet was assessed radiographically by the change from baseline in the van der Heijde-Sharp (vdH-S) score, modified by the addition of hand DIP joints. The total modified vdH-S score is a composite score of structural damage that measures the number and size of joint erosions and the degree of joint space narrowing (JSN) in the hands and feet. At Week 24, patients treated with infliximab had less radiographic progression than placebo-treated patients (mean change of -0.70 vs. 0.82, P<0.001). Patients treated with infliximab also had less progression in their erosion scores (-0.56 vs 0.51) and JSN scores (-0.14 vs 0.31). The patients in the infliximab group demonstrated continued inhibition of structural damage at Week 54. Most patients showed little or no change in the vdH-S score during this 12-month study (median change of 0 in both patients who initially received infliximab or placebo). More patients in the placebo group (12%) had readily apparent radiographic progression compared with the infliximab group (3%).

Physical Function

Physical function status was assessed using the HAQ Disability Index (HAQ-DI) and the SF-36 Health Survey. Patients treated with infliximab demonstrated significant improvement in physical function as assessed by HAQ-DI (median percent improvement in HAQ-DI score from baseline to Week 14 and 24 of 43% for infliximab-treated patients vs 0% for placebo-treated patients).

During the placebo-controlled portion of the trial (24 weeks), 54% of patients treated with infliximab achieved a clinically meaningful improvement in HAQ-DI (≥0.3 unit decrease) compared to 22% of placebo-treated patients. Patients treated with infliximab also demonstrated greater improvement in the SF-36 physical and mental component summary scores than placebo-treated patients. The responses were maintained for up to 2 years in an open-label extension study.

14.8 Plaque Psoriasis

The safety and efficacy of infliximab were assessed in 3 randomized, double-blind, placebo-controlled studies in patients 18 years of age and older with chronic, stable Ps involving ≥10% BSA, a minimum PASI score of 12, and who were candidates for systemic therapy or phototherapy. Patients with guttate, pustular, or erythrodermic psoriasis were excluded from these studies. No concomitant anti-psoriatic therapies were allowed during the study, with the exception of low-potency topical corticosteroids on the face and groin after Week 10 of study initiation.

Study I (EXPRESS) evaluated 378 patients who received placebo or infliximab at a dose of 5 mg/kg at Weeks 0, 2, and 6 (induction therapy), followed by maintenance therapy every 8 weeks. At Week 24, the placebo group crossed over to infliximab induction therapy (5 mg/kg), followed by maintenance therapy every 8 weeks. Patients originally randomized to infliximab continued to receive infliximab 5 mg/kg every 8 weeks through Week 46. Across all treatment groups, the median baseline PASI score was 21 and the baseline Static Physician Global Assessment (sPGA) score ranged from moderate (52% of patients) to marked (36%) to severe (2%). In addition, 75% of patients had a BSA >20%. Seventy-one percent of patients previously received systemic therapy, and 82% received phototherapy.

Study II (EXPRESS II) evaluated 835 patients who received placebo or infliximab at doses of 3 mg/kg or 5 mg/kg at Weeks 0, 2, and 6 (induction therapy). At Week 14, within each infliximab dose group, patients were randomized to either scheduled (every 8 weeks) or as needed (PRN) maintenance treatment through Week 46. At Week 16, the placebo group crossed over to infliximab induction therapy (5 mg/kg), followed by maintenance therapy every 8 weeks. Across all treatment groups, the median baseline PASI score was 18, and 63% of patients had a BSA >20%. Fifty-five percent of patients previously received systemic therapy, and 64% received a phototherapy.

Study III (SPIRIT) evaluated 249 patients who had previously received either psoralen plus ultraviolet A treatment (PUVA) or other systemic therapy for their psoriasis. These patients were randomized to receive either placebo or infliximab at doses of 3 mg/kg or 5 mg/kg at Weeks 0, 2, and 6. At Week 26, patients with a sPGA score of moderate or worse (greater than or equal to 3 on a scale of 0 to 5) received an additional dose of the randomized treatment. Across all treatment groups, the median baseline PASI score was 19, and the baseline sPGA score ranged from moderate (62% of patients) to marked (22%) to severe (3%). In addition, 75% of patients had a BSA >20%. Of the enrolled patients, 114 (46%) received the Week 26 additional dose.

In Studies I, II and III, the primary endpoint was the proportion of patients who achieved a reduction in score of at least 75% from baseline at Week 10 by the PASI (PASI 75). In Study I and Study III, another evaluated outcome included the proportion of patients who achieved a score of "cleared" or "minimal" by the sPGA. The sPGA is a 6-category scale ranging from "5 = severe" to "0 = cleared" indicating the physician's overall assessment of the psoriasis severity focusing on induration, erythema, and scaling. Treatment success, defined as "cleared" or "minimal," consisted of none or minimal elevation in plaque, up to faint red coloration in erythema, and none or minimal fine scale over <5% of the plaque.

Study II also evaluated the proportion of patients who achieved a score of "clear" or "excellent" by the relative Physician's Global Assessment (rPGA). The rPGA is a 6-category scale ranging from "6 = worse" to "1 = clear" that was assessed relative to baseline. Overall lesions were graded with consideration to the percent of body involvement as well as overall induration, scaling, and erythema. Treatment success, defined as "clear" or "excellent," consisted of some residual pinkness or pigmentation to marked improvement (nearly normal skin texture; some erythema may be present). The results of these studies are presented in Table 12.

Table 12 Adult Psoriasis Studies I, II, and III, Percentage of Patients who Achieved PASI75 and Percentage who Achieved Treatment "Success" with Physician's Global Assessment at Week 10
 | Placebo | Infliximab
 |  | 3 mg/kg | 5 mg/kg
Psoriasis Study I - patients randomized [Patients with missing data at Week 10 were considered as nonresponders.] | 77 | --- | 301
PASI 75 | 2 (3%) | --- | 242 (80%) [P<0.001 compared with placebo]
sPGA | 3 (4%) | --- | 242 (80%)
Psoriasis Study II - patients randomized | 208 | 313 | 314
PASI 75 | 4 (2%) | 220 (70%) | 237 (75%)
rPGA | 2 (1%) | 217 (69%) | 234 (75%)
Psoriasis Study III - patients randomized [Patients with missing data at Week 10 were imputed by last observation.] | 51 | 99 | 99
PASI 75 | 3 (6%) | 71 (72%) | 87 (88%)
sPGA | 5 (10%) | 71 (72%) | 89 (90%)

In Study I, in the subgroup of patients with more extensive Ps who had previously received phototherapy, 85% of patients on 5 mg/kg infliximab achieved a PASI 75 at Week 10 compared with 4% of patients on placebo.

In Study II, in the subgroup of patients with more extensive Ps who had previously received phototherapy, 72% and 77% of patients on 3 mg/kg and 5 mg/kg infliximab achieved a PASI 75 at Week 10 respectively compared with 1% on placebo. In Study II, among patients with more extensive Ps who had failed or were intolerant to phototherapy, 70% and 78% of patients on 3 mg/kg and 5 mg/kg infliximab achieved a PASI 75 at Week 10 respectively, compared with 2% on placebo.

Maintenance of response was studied in a subset of 292 and 297 patients treated with infliximab in the 3 mg/kg and 5 mg/kg groups; respectively, in Study II. Stratified by PASI response at Week 10 and investigational site, patients in the active treatment groups were re-randomized to either a scheduled or as needed maintenance (PRN) therapy, beginning on Week 14.

The groups that received a maintenance dose every 8 weeks appear to have a greater percentage of patients maintaining a PASI 75 through week 50 as compared to patients who received the as-needed or PRN doses, and the best response was maintained with the 5 mg/kg every 8-week dose. These results are shown in Figure 4. At Week 46, when infliximab serum concentrations were at trough level, in the every 8-week dose group, 54% of patients in the 5 mg/kg group compared to 36% in the 3 mg/kg group achieved PASI 75. The lower percentage of PASI 75 responders in the 3 mg/kg every 8-week dose group compared to the 5 mg/kg group was associated with a lower percentage of patients with detectable trough serum infliximab levels.

This may be related in part to higher antibody rates [see Adverse Reactions (6.1)]. In addition, in a subset of patients who had achieved a response at Week 10, maintenance of response appears to be greater in patients who received infliximab every 8 weeks at the 5 mg/kg dose. Regardless of whether the maintenance doses are PRN or every 8 weeks, there is a decline in response in a subpopulation of patients in each group over time. The results of Study I through Week 50 in the 5 mg/kg every 8 weeks maintenance dose group were similar to the results from Study II.

Figure 4 Proportion of Adult Ps Patients Who Achieved ≥75% Improvement in PASI from Baseline through Week 50 (patients randomized at Week 14)

Efficacy and safety of infliximab treatment beyond 50 weeks have not been evaluated in patients with Ps.

15 REFERENCES

1. Turner D, Otley AR, Mack D, et al. Development, validation, and evaluation of a pediatric ulcerative colitis activity index: A prospective multicenter study. Gastroenterology. 2007;133:423–432.

16 HOW SUPPLIED/STORAGE AND HANDLING

How Supplied

INFLECTRA (infliximab-dyyb) for injection is supplied as one single-dose vial individually packaged in a carton (NDC 0069-0809-01 100 mg vial).

Each single-dose vial contains 100 mg of infliximab-dyyb as a sterile, preservative-free, white lyophilized powder for reconstitution and dilution (more than one vial may be needed for a full dose) [see Dosage and Administration (2.11)].

Storage and Handling

Store unopened INFLECTRA® vials in a refrigerator at 2°C to 8°C (36°F to 46°F).

If needed, unopened INFLECTRA vials may be stored at room temperature up to a maximum of 30°C (86°F) for a single period up to 6 months but not exceeding the original expiration date. The new expiration date must be written in the space provided on the carton. Once removed from the refrigerator, INFLECTRA cannot be returned to the refrigerator.

Not made with natural rubber latex.

For storage condition of the reconstituted and diluted product for administration, see Dosage and Administration (2.11).

17 PATIENT COUNSELING INFORMATION

Advise the patient or their caregiver to read the FDA-Approved Patient Labeling (Medication Guide).

Patients or their caregivers should be advised of the potential benefits and risks of INFLECTRA. Healthcare providers should instruct their patients or their caregivers to read the Medication Guide before starting INFLECTRA therapy and to reread it each time they receive an infusion.

Infections

Inform patients that INFLECTRA increases the risk for developing serious infections. Instruct patients of the importance of contacting their healthcare provider if they develop any symptoms of an infection, including tuberculosis, invasive fungal infections, and reactivation of hepatitis B virus infections [see Warnings and Precautions (5.1, 5.3)].

Malignancies

Malignancies have been reported among children, adolescents and young adults who received treatment with TNF blockers. Patients should be counseled about the risk of lymphoma and other malignancies while receiving INFLECTRA [see Warnings and Precautions (5.2)].

Hepatotoxicity

Instruct patients to seek medical attention if they develop signs or symptoms of hepatotoxicity (e.g., jaundice) [see Warnings and Precautions (5.4)].

Heart Failure

Instruct patients to seek medical attention and consult their prescriber if they develop signs or symptoms of heart failure [see Contraindications (4) and Warnings and Precautions (5.5)].

Hematologic Reactions

Instruct patients to seek immediate medical attention if they develop signs and symptoms suggestive of blood dyscrasias or infection (e.g., persistent fever) while on INFLECTRA [see Warnings and Precautions (5.6)].

Hypersensitivity

Advise patients to seek immediate medical attention if they experience any symptoms of serious hypersensitivity reactions [see Warnings and Precautions (5.7)].

Cardiovascular and Cerebrovascular Reactions During and After Infusion

Advise patients to seek immediate medical attention if they develop any new or worsening symptoms of cardiovascular and cerebrovascular reactions which have been reported during and within 24 hours of initiation of INFLECTRA infusion [see Warnings and Precautions (5.8)].

Neurologic Reactions

Advise patients to seek medical attention if they develop signs or symptoms of neurologic reactions [see Warnings and Precautions (5.9)].

Live Vaccines/Therapeutic Infectious Agents

Instruct INFLECTRA-treated patients to avoid receiving live vaccines or therapeutic infectious agents [see Warnings and Precautions (5.13)].

Manufactured by:
CELLTRION, Inc.
23, Academy-ro,
Yeonsu-gu, Incheon
22014, Republic of Korea
U.S. License No. 1996

Distributed by
Pfizer Labs
Division of Pfizer Inc.
New York, NY 10001

©CELLTRION, Inc.

MEDICATION GUIDE
INFLECTRA® (In-flec-tra)
(infliximab-dyyb)
for injection, for intravenous use

Read the Medication Guide that comes with INFLECTRA before you receive the first treatment, and before each time you get a treatment of INFLECTRA. This Medication Guide does not take the place of talking with your doctor about your medical condition or treatment.
What is the most important information I should know about INFLECTRA?
INFLECTRA may cause serious side effects, including:
1. Risk of infection
INFLECTRA is a medicine that affects your immune system. INFLECTRA can lower the ability of your immune system to fight infections. Serious infections have happened in patients receiving INFLECTRA. These infections include tuberculosis (TB) and infections caused by viruses, fungi, or bacteria that have spread throughout the body. Some patients have died from these infections.

- Your doctor should test you for TB before starting INFLECTRA.
- Your doctor should monitor you closely for signs and symptoms of TB during treatment with INFLECTRA.

Before starting INFLECTRA, tell your doctor if you:

- think you have an infection. You should not start receiving INFLECTRA if you have any kind of infection.
- are being treated for an infection.
- have signs of an infection, such as a fever, cough, flu-like symptoms.
- have any open cuts or sores on your body.
- get a lot of infections or have infections that keep coming back.
- have diabetes or an immune system problem. People with these conditions have a higher chance for infections.
- have TB, or have been in close contact with someone with TB.
- live or have lived in certain parts of the country (such as the Ohio and Mississippi River valleys) where there is an increased risk for getting certain kinds of fungal infections (histoplasmosis, coccidioidomycosis, or blastomycosis). These infections may develop or become more severe if you receive INFLECTRA. If you do not know if you have lived in an area where histoplasmosis, coccidioidomycosis, or blastomycosis is common, ask your doctor.
- have or have had hepatitis B.
- use the medicines KINERET (anakinra), ORENCIA (abatacept), ACTEMRA (tocilizumab), or other medicines called biologics used to treat the same conditions as INFLECTRA.

After starting INFLECTRA, if you have an infection, any sign of an infection including a fever, cough, flu-like symptoms, or have open cuts or sores on your body, call your doctor right away. INFLECTRA can make you more likely to get infections or make any infection that you have worse.
2. Risk of Cancer

- There have been cases of unusual cancers in children and teenage patients using tumor necrosis factor (TNF) blocker medicines, such as INFLECTRA.
- For children and adults receiving TNF blocker medicines, including INFLECTRA, the chances of getting lymphoma or other cancers may increase.
- Some people receiving TNF blockers, including INFLECTRA, developed a rare type of cancer called hepatosplenic T-cell lymphoma. This type of cancer often results in death. Most of these people were male teenagers or young men. Also, most people were being treated for Crohn's disease or ulcerative colitis with a TNF blocker and another medicine called azathioprine or 6-mercaptopurine.
- People who have been treated for rheumatoid arthritis, Crohn's disease, ulcerative colitis, ankylosing spondylitis, psoriatic arthritis and plaque psoriasis for a long time may be more likely to develop lymphoma. This is especially true for people with very active disease.
- Some people treated with infliximab products, such as INFLECTRA, have developed certain kinds of skin cancer. If any changes in the appearance of your skin or growths on your skin occur during or after your treatment with INFLECTRA, tell your doctor.
- Patients with Chronic Obstructive Pulmonary Disease (COPD), a specific type of lung disease, may have an increased risk for getting cancer while being treated with INFLECTRA.
- Some women being treated for rheumatoid arthritis with infliximab products have developed cervical cancer. For women receiving INFLECTRA, including those over 60 years of age, your doctor may recommend that you continue to be regularly screened for cervical cancer.
- Tell your doctor if you have ever had any type of cancer. Discuss with your doctor any need to adjust medicines you may be taking.

See the section "What are the possible side effects of INFLECTRA?" below for more information.

What is INFLECTRA?
INFLECTRA is a prescription medicine that is approved for patients with:

- Rheumatoid Arthritis - adults with moderately to severely active rheumatoid arthritis, along with the medicine methotrexate.
- Crohn's Disease - children 6 years and older and adults with Crohn's disease who have not responded well to other medicines.
- Ankylosing Spondylitis in adults
- Psoriatic Arthritis in adults
- Plaque Psoriasis - adult patients with plaque psoriasis that is chronic (does not go away) severe, extensive, and/or disabling.
- Ulcerative Colitis – children 6 years and older and adults with moderately to severely active ulcerative colitis who have not responded well to other medicines.

INFLECTRA blocks the action of a protein in your body called tumor necrosis factor-alpha (TNF-alpha). TNF-alpha is made by your body's immune system. People with certain diseases have too much TNF-alpha that can cause the immune system to attack normal healthy parts of the body. INFLECTRA can block the damage caused by too much TNF-alpha.
It is not known if INFLECTRA is safe and effective in children under 6 years of age.

Who should not receive INFLECTRA?
You should not receive INFLECTRA if you have:

- heart failure, unless your doctor has examined you and decided that you are able to receive INFLECTRA. Talk to your doctor about your heart failure.
- had an allergic reaction to infliximab products or any of the ingredients in INFLECTRA. See the end of this Medication Guide for a complete list of ingredients in INFLECTRA.

What should I tell my doctor before starting treatment with INFLECTRA?
Your doctor will assess your health before each treatment.
Tell your doctor about all of your medical conditions, including if you:

- have an infection (see "What is the most important information I should know about INFLECTRA?").
- have other liver problems including liver failure.
- have heart failure or other heart conditions. If you have heart failure, it may get worse while you receive INFLECTRA.
- have or have had any type of cancer.
- have had phototherapy (treatment with ultraviolet light or sunlight along with a medicine to make your skin sensitive to light) for psoriasis. You may have a higher chance of getting skin cancer while receiving INFLECTRA.
- have COPD (Chronic Obstructive Pulmonary Disease), a specific type of lung disease. Patients with COPD may have an increased risk of getting cancer while receiving INFLECTRA.
- have or have had a condition that affects your nervous system such as:
  - multiple sclerosis, or Guillain-Barré syndrome, or
  - if you experience any numbness or tingling, or
  - if you have had a seizure.
- have recently received or are scheduled to receive a vaccine. Adults and children receiving INFLECTRA should not receive live vaccines (for example, the Bacille Calmette-Guérin [BCG] vaccine) or treatment with a weakened bacteria (such as BCG for bladder cancer). Adults and children should have all of their vaccines brought up to date before starting treatment with INFLECTRA.
- are pregnant or plan to become pregnant, are breastfeeding or plan to breastfeed. You and your doctor should decide if you should receive INFLECTRA while you are pregnant or breastfeeding.

If you have a baby and you were receiving INFLECTRA during your pregnancy, it is important to tell your baby's doctor and other healthcare professionals about your INFLECTRA use so they can decide when your baby should receive any vaccine. Certain vaccinations can cause infections.
If you received INFLECTRA while you were pregnant, your baby may be at higher risk for getting an infection. If your baby receives a live vaccine within 6 months after birth, your baby may develop infections with serious complications that can lead to death. This includes live vaccines such as the BCG, rotavirus, or any other live vaccines. For other types of vaccines, talk with your doctor.

How should I receive INFLECTRA?

- You will be given INFLECTRA through a needle placed in a vein (IV or intravenous infusion) in your arm.
- Your doctor may decide to give you medicine before starting the INFLECTRA infusion to prevent or lessen side effects.
- Only a healthcare professional should prepare the medicine and administer it to you.
- INFLECTRA will be given to you over a period of about 2 hours.
- If you have side effects from INFLECTRA, the infusion may need to be adjusted or stopped. In addition, your healthcare professional may decide to treat your symptoms.
- A healthcare professional will monitor you during the INFLECTRA infusion and for a period of time afterward for side effects. Your doctor may do certain tests while you are receiving INFLECTRA to monitor you for side effects and to see how well you respond to the treatment.
- Your doctor will determine the right dose of INFLECTRA for you and how often you should receive it. Make sure to discuss with your doctor when you will receive infusions and to come in for all your infusions and follow-up appointments.

What should I avoid while receiving INFLECTRA?
Do not take INFLECTRA together with medicines such as KINERET (anakinra), ORENCIA (abatacept), ACTEMRA (tocilizumab), or other medicines called biologics that are used to treat the same conditions as INFLECTRA.
Tell your doctor about all the medicines you take, including prescription and over-the-counter medicines, vitamins, and herbal supplements. These include any other medicines to treat Crohn's disease, ulcerative colitis, rheumatoid arthritis, ankylosing spondylitis, psoriatic arthritis or psoriasis.
Know the medicines you take. Keep a list of your medicines and show them to your doctor and pharmacist when you get a new medicine.

What are the possible side effects of INFLECTRA?
INFLECTRA can cause serious side effects, including:
See "What is the most important information I should know about INFLECTRA?".
Serious Infections

- Some patients, especially those 65 years and older have had serious infections while receiving infliximab products, such as INFLECTRA. These serious infections include TB and infections caused by viruses, fungi, or bacteria that have spread throughout the body or cause infections in certain areas (such as skin). Some patients die from these infections. If you get an infection while receiving treatment with INFLECTRA your doctor will treat your infection and may need to stop your INFLECTRA treatment.
- Tell your doctor right away if you have any of the following signs of an infection while receiving or after receiving INFLECTRA:

- a fever
- feel very tired
- have a cough

- have flu-like symptoms
- warm, red, or painful skin

- Your doctor will examine you for TB and perform a test to see if you have TB. If your doctor feels that you are at risk for TB, you may be treated with medicine for TB before you begin treatment with INFLECTRA and during treatment with INFLECTRA.
- Even if your TB test is negative, your doctor should carefully monitor you for TB infections while you are receiving INFLECTRA. Patients who had a negative TB skin test before receiving infliximab products have developed active TB.
- If you are a chronic carrier of the hepatitis B virus, the virus can become active while you are being treated with INFLECTRA. In some cases, patients have died as a result of hepatitis B virus being reactivated. Your doctor should do a blood test for hepatitis B virus before you start treatment with INFLECTRA and occasionally while you are being treated. Tell your doctor if you have any of the following symptoms:

- feel unwell
- poor appetite

- tiredness (fatigue)
- fever, skin rash, or joint pain

Heart Failure
If you have a heart problem called congestive heart failure, your doctor should check you closely while you are receiving INFLECTRA. Your congestive heart failure may get worse while you are receiving INFLECTRA. Be sure to tell your doctor of any new or worse symptoms including:

- shortness of breath
- swelling of ankles or feet

- sudden weight gain

Treatment with INFLECTRA may need to be stopped if you get new or worse congestive heart failure.
Other Heart Problems
Some patients have experienced a heart attack (some of which led to death), low blood flow to the heart, or abnormal heart rhythm within 24 hours of beginning their infusion of infliximab products. Symptoms may include chest discomfort or pain, arm pain, stomach pain, shortness of breath, anxiety, lightheadedness, dizziness, fainting, sweating, nausea, vomiting, fluttering or pounding in your chest, and/or a fast or a slow heartbeat. Tell your doctor right away if you have any of these symptoms.
Liver Injury
Some patients receiving infliximab products have developed serious liver problems. Tell your doctor if you have:

- jaundice (skin and eyes turning yellow)
- dark brown-colored urine
- pain on the right side of your stomach area (right-sided abdominal pain)

- fever
- extreme tiredness (severe fatigue)

Blood Problems
In some patients receiving infliximab products, the body may not make enough of the blood cells that help fight infections or help stop bleeding. Tell your doctor if you:

- have a fever that does not go away
- bruise or bleed very easily

- look very pale

Nervous System Disorders
Some patients receiving infliximab products have developed problems with their nervous system. Tell your doctor if you have:

- changes in your vision
- numbness or tingling in any part of your body

- seizures
- weakness in your arms or legs

Some patients have experienced a stroke within approximately 24 hours of their infusion with infliximab products. Tell your doctor right away if you have symptoms of a stroke which may include: numbness or weakness of the face, arm or leg, especially on one side of the body; sudden confusion, trouble speaking or understanding; sudden trouble seeing in one or both eyes, sudden trouble walking, dizziness, loss of balance or coordination or a sudden, severe headache.
Allergic Reactions
Some patients have had allergic reactions to infliximab products. Some of these reactions were severe. These reactions can happen while you are getting your INFLECTRA treatment or shortly afterward. Your doctor may need to stop or pause your treatment with INFLECTRA and may give you medicines to treat the allergic reaction. Signs of an allergic reaction can include:

- hives (red, raised, itchy patches of skin)
- difficulty breathing
- chest pain

- high or low blood pressure
- fever
- chills

Some patients treated with infliximab products have had delayed allergic reactions. The delayed reactions occurred within 3 to 12 days after receiving treatment with infliximab products. Tell your doctor right away if you have any of these signs of delayed allergic reaction to INFLECTRA:

- fever
- rash
- headache
- sore throat

- muscle or joint pain
- swelling of the face and hands
- difficulty swallowing

Lupus-like Syndrome
Some patients have developed symptoms that are like the symptoms of Lupus. If you develop any of the following symptoms, your doctor may decide to stop your treatment with INFLECTRA.

- chest discomfort or pain that does not go away
- shortness of breath

- joint pain
- rash on the cheeks or arms that gets worse in the sun

Psoriasis
Some people receiving infliximab products had new psoriasis or worsening of psoriasis they already had. Tell your doctor if you develop red scaly patches or raised bumps on the skin that are filled with pus. Your doctor may decide to stop your treatment with INFLECTRA.
The most common side effects of infliximab products include:

- respiratory infections, such as sinus infections and sore throat
- headache

- coughing
- stomach pain

Infusion reactions can happen up to 2 hours after your infusion of INFLECTRA. Symptoms of infusion reactions may include:

- fever
- chills
- chest pain

- low blood pressure or high blood pressure
- shortness of breath

- rash
- itching

Children with Crohn's disease who received infliximab showed some differences in side effects of treatment compared with adults with Crohn's disease. The side effects that happened more in children were: anemia (low red blood cells), leukopenia (low white blood cells), flushing (redness or blushing), viral infections, neutropenia (low neutrophils, the white blood cells that fight infection), bone fracture, bacterial infection and allergic reactions of the breathing tract. Among patients who received infliximab for ulcerative colitis in clinical studies, more children had infections as compared with adults.
Tell your doctor about any side effect that bothers you or does not go away.
These are not all of the side effects with INFLECTRA. Ask your doctor or pharmacist for more information.
Call your doctor for medical advice about side effects. You may report side effects to FDA at 1-800-FDA-1088.

General information about INFLECTRA
Medicines are sometimes prescribed for purposes other than those listed in a Medication Guide.
You can ask your doctor or pharmacist for information about INFLECTRA that is written for health professionals.
For more information go to www.pfizer.com or call 1-800-383-7504.

What are the ingredients in INFLECTRA?
The active ingredient is infliximab-dyyb.
The inactive ingredients in INFLECTRA include: dibasic sodium phosphate dihydrate, monobasic sodium phosphate monohydrate, polysorbate 80, and sucrose. No preservatives are present.
Not made with natural rubber latex.

Manufactured by: CELLTRION, Inc. 23, Academy-ro, Yeonsu-gu, Incheon, 22014, Republic of Korea
U.S. License No. 1996 ©CELLTRION, Inc.
Distributed by Pfizer Labs, Division of Pfizer Inc., New York, NY 10001
For more information go to www.pfizer.com or call 1-800-383-7504.

This Medication Guide has been approved by the U.S. Food and Drug Administration Revised: September 2025

PRINCIPAL DISPLAY PANEL - 100 mg Vial Label

NDC 0069-0809-01

Inflectra®
(infliximab-dyyb)
For Injection

100 mg per vial

For Intravenous
Infusion Only
Single-dose vial
Discard unused portion
Rx only

PRINCIPAL DISPLAY PANEL - 100 mg Vial Carton

NDC 0069-0809-01

Inflectra®
(infliximab-dyyb)
For Injection

100 mg per vial

For Intravenous Infusion Only
Single-dose vial
Discard unused portion
Dispense the enclosed
Medication Guide to each patient.
Reconstitute and Dilute Before
Intravenous Infusion.
Infuse over at least 2 hours with an
in-line filter.

Rx only

Pfizer